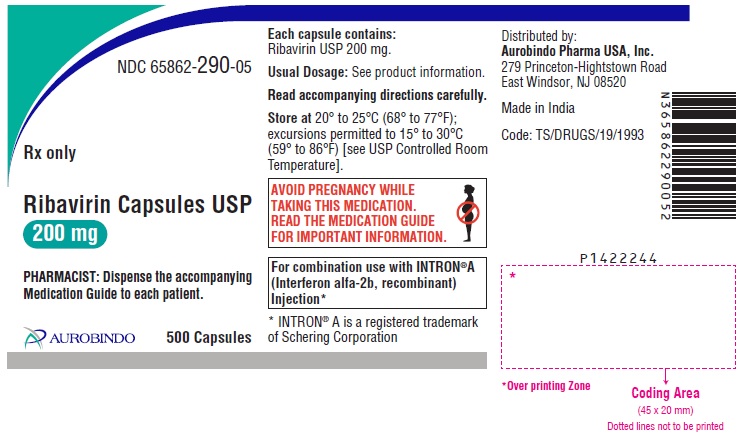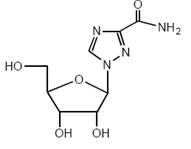 DRUG LABEL: Ribavirin
NDC: 65862-290 | Form: CAPSULE
Manufacturer: Aurobindo Pharma Limited
Category: prescription | Type: Human Prescription Drug Label
Date: 20240206

ACTIVE INGREDIENTS: RIBAVIRIN 200 mg/1 1
INACTIVE INGREDIENTS: MICROCRYSTALLINE CELLULOSE; LACTOSE MONOHYDRATE; POVIDONE K30; MAGNESIUM STEARATE; TITANIUM DIOXIDE; SODIUM LAURYL SULFATE; GELATIN, UNSPECIFIED; FERROSOFERRIC OXIDE

HIGHLIGHTS OF PRESCRIBING INFORMATION

These highlights do not include all the information needed to use RIBAVIRIN CAPSULES safely and effectively. See full prescribing information for RIBAVIRIN CAPSULES.
RIBAVIRIN capsules, for oral use
Initial U.S. Approval: 1998

WARNING: EMBRYO-FETAL TOXICITY, HEMOLYTIC ANEMIA, and MONOTHERAPY NOT RECOMMENDED

WARNING: EMBRYO-FETAL TOXICITY, HEMOLYTIC

ANEMIA, and MONOTHERAPY NOT RECOMMENDED

See full prescribing information for complete boxed warning.

- Significant teratogenic and embryocidal effects have been demonstrated in all animal species exposed to ribavirin. Therefore, ribavirin therapy is contraindicated in women who are pregnant and in the male partners of women who are pregnant. Avoid pregnancy during therapy and for 9 months after completion of treatment in female patients and for 6 months in female partners of male patients who are taking ribavirin therapy. (4, 5.1, 8.1, 8.3, 13.1)

The hemolytic anemia associated with ribavirin therapy may result in worsening of cardiac disease that has led to fatal and nonfatal myocardial infarctions. Patients with a history of significant or unstable cardiac disease should not be treated with ribavirin. (2.5, 5.2, 6.1)

- Ribavirin monotherapy is not effective for the treatment of chronic hepatitis C. (5.10)

1 INDICATIONS AND USAGE

Ribavirin capsules are a nucleoside analogue indicated in combination with interferon alfa-2b (pegylated and nonpegylated) for the treatment of Chronic Hepatitis C (CHC) in patients 3 years of age or older with compensated liver disease. (1.1)

Patients with the following characteristics are less likely to benefit from re-treatment after failing a course of therapy: previous nonresponse, previous pegylated interferon treatment, significant bridging fibrosis or cirrhosis, and genotype 1 infection.

2 DOSAGE AND ADMINISTRATION

Ribavirin capsules are administered according to body weight. (2.1, 2.2, 2.3)

Dose reduction or discontinuation is recommended in patients experiencing certain adverse reactions or renal dysfunction. (2.5, 2.6, 12.3)

3 DOSAGE FORMS AND STRENGTHS

- Ribavirin Capsules USP 200 mg (3)

4 CONTRAINDICATIONS

- Pregnancy and men whose female partners are pregnant (4, 5.1, 8.1, 8.3)
- Known hypersensitivity reactions such as Stevens-Johnson syndrome, toxic, epidermal necrolysis, and erythema multiforme to ribavirin or any component of the product (4)
- Autoimmune hepatitis (4)
- Hemoglobinopathies (4)
- Creatinine clearance less than 50 mL/min (4, 12.3)
- Coadministration with didanosine (4, 7.1)

5 WARNINGS AND PRECAUTIONS

- Embryo-Fetal Toxicity: May cause fetal harm. Patients should have a negative pregnancy test prior to therapy and use effective contraception and undergo periodic pregnancy tests. (5.1, 8.1, 8.3)

Patients exhibiting the following conditions should be closely monitored and may require dose reduction or discontinuation of therapy:

- Hemolytic anemia may occur with a significant initial drop in hemoglobin. (5.2)
- Pancreatitis. (5.3)
- Pulmonary infiltrates or pulmonary function impairment. (5.4)
- New or worsening ophthalmologic disorders. (5.5)
- Severe decreases in neutrophil and platelet counts, and hematologic, endocrine (e.g., TSH), and hepatic abnormalities. (5.6)
- Dental/periodontal disorders reported with combination therapy. (5.7)
- Concomitant administration of azathioprine. (5.8)
- Weight loss and growth inhibition reported during combination therapy in pediatric patients. Long-term growth inhibition (height) reported in some patients. (5.9)
- Monotherapy with ribavirin is not permitted. (5.10)

6 ADVERSE REACTIONS

Hemolytic anemia occurred in more than 10% of adult patients receiving ribavirin/PegIntron or INTRON A combination therapy. (6.1)

Most common adverse reactions (40% or greater) in adult patients receiving ribavirin/PegIntron or INTRON A combination therapy are injection site reaction, fatigue/asthenia, headache, rigors, fevers, nausea, myalgia and anxiety/emotional lability/irritability. (6.1) Most common adverse reactions (greater than 25%) in pediatric patients receiving ribavirin/PegIntron therapy are: pyrexia, headache, neutropenia, fatigue, anorexia, injection site erythema, and vomiting. (6.1)

To report SUSPECTED ADVERSE REACTIONS, contact Aurobindo Pharma USA, Inc. at 1-866-850-2876 or FDA at 1-800-FDA-1088 or www.fda.gov/medwatch.

7 DRUG INTERACTIONS

Nucleoside analogues: Closely monitor for toxicities. Discontinue nucleoside reverse transcriptase inhibitors or reduce dose or discontinue interferon, ribavirin or both with worsening toxicities. (7.2)

8 USE IN SPECIFIC POPULATIONS

- Pediatrics: Safety and efficacy in patients less than 3 years old have not been established. (8.4)
- Organ transplant recipients: Safety and efficacy not studied. (8.6)
- Co-infected patients: Safety and efficacy with HIV or HBV co-infection have not been established. (8.7)

FULL PRESCRIBING INFORMATION

WARNING: EMBRYO-FETAL TOXICITY, HEMOLYTIC ANEMIA, and MONOTHERAPY NOT RECOMMENDED

- Significant teratogenic and embryocidal effects have been demonstrated in all animal species exposed to ribavirin. In addition, ribavirin has a multiple-dose half-life of 12 days and may persist in non-plasma compartments for as long as 6 months. Therefore, ribavirin therapy is contraindicated in women who are pregnant and in the male partners of women who are pregnant. Avoid pregnancy and use effective contraception during therapy and for 9 months after completion of treatment in female patients and for 6 months in female partners of male patients who are taking ribavirin therapy. [see Contraindications (4), Warnings and Precautions (5.1), Use in Specific Populations (8.1, 8.3), and Nonclinical Toxicology (13.1)].
- Hemolytic anemia has been reported with ribavirin therapy. The anemia associated with ribavirin therapy may result in worsening of cardiac disease that has led to fatal and nonfatal myocardial infarctions. Patients with a history of significant or unstable cardiac disease should not be treated with ribavirin [see Dosage and Administration (2.5), Warnings and Precautions (5.2), and Adverse Reactions (6.1)].
- Ribavirin monotherapy is not effective for the treatment of chronic hepatitis C virus infection and should not be used alone for this indication [see Warnings and Precautions (5.10)].

1 INDICATIONS AND USAGE

1.1 Chronic Hepatitis C (CHC)

Ribavirin capsules in combination with interferon alfa-2b (pegylated and nonpegylated) are indicated for the treatment of Chronic Hepatitis C (CHC) in patients 3 years of age and older with compensated liver disease [see Warnings and Precautions (5.9, 5.10), and Use in Specific Populations (8.4)].

The following points should be considered when initiating ribavirin capsules combination therapy with PegIntron® or INTRON A®:

- Combination therapy with ribavirin capsules/PegIntron is preferred over ribavirin capsules/INTRON A as this combination provides substantially better response rates [see Clinical Studies (14)].
- Patients with the following characteristics are less likely to benefit from re-treatment after failing a course of therapy: previous nonresponse, previous pegylated interferon treatment, significant bridging fibrosis or cirrhosis, and genotype 1 infection [see Clinical Studies (14)].
- No safety and efficacy data are available for treatment duration lasting longer than one year.

2 DOSAGE AND ADMINISTRATION

2.1 General Dosing Information

Do not open, crush or break ribavirin capsules. Ribavirin capsules should be taken with food [see Clinical Pharmacology (12.3)].

2.2 Ribavirin capsules/PegIntron Combination Therapy

Adult Patients

The recommended dose of ribavirin capsules when used in combination with PegIntron is 800 mg to 1,400 mg based on patient body weight in two divided doses (see Table 1). Refer to PegIntron labeling for PegIntron dosing information.

Duration of Treatment – Interferon Alpha-naïve Patients
The treatment duration for patients with genotype 1 is 48 weeks. Discontinuation of therapy should be considered in patients who do not achieve at least a 2 log10 drop or loss of hepatitis C virus (HCV)-RNA at 12 weeks, or if HCV-RNA remains detectable after 24 weeks of therapy. Patients with genotype 2 and 3 should be treated for 24 weeks.
Duration of Treatment – Re-treatment with PegIntron/Ribavirin capsules of Prior Treatment Failures
The treatment duration for patients who previously failed therapy is 48 weeks, regardless of HCV genotype. Re-treated patients who fail to achieve undetectable HCV-RNA at Week 12 of therapy, or whose HCV-RNA remains detectable after 24 weeks of therapy, are highly unlikely to achieve SVR and discontinuation of therapy should be considered [see Clinical Studies (14.1)].

Table 1: Recommended Adult Dosing for Ribavirin capsules in Combination with PegIntron
Body Weight (kg) | Ribavirin capsules Daily Dose | Ribavirin Number of Capsules
Less than 66 | 800 mg/day | 2 x 200 mg capsules AM 2 x 200 mg capsules PM
66 to 80 | 1,000 mg/day | 2 x 200 mg capsules AM 3 x 200 mg capsules PM
81 to 105 | 1,200 mg/day | 3 x 200 mg capsules AM 3 x 200 mg capsules PM
Greater than 105 | 1,400 mg/day | 3 x 200 mg capsules AM 4 x 200 mg capsules PM

Pediatric Patients
Dosing of ribavirin in pediatric patients is determined by body weight. The recommended dose of ribavirin when used in combination with PegIntron in pediatric patients ages 3 to 17 years is 15 mg/kg/day in two divided doses (see Table 2). Refer to PegIntron labeling for PegIntron dosing information. The treatment duration for patients with genotype 1 is 48 weeks. Patients with genotype 2 and 3 should be treated for 24 weeks.

Table 2: Recommended Pediatric Ribavirin Dosing in Combination with PegIntron
Body Weight (kg) | Ribavirin Daily Dose | Ribavirin Number of Capsules
Less than 47 | 15 mg/kg/day | Use Ribavirin Oral Solution*
47 to 59 | 800 mg/day | 2 x 200 mg capsules AM 2 x 200 mg capsules PM
60 to 73 | 1,000 mg/day | 2 x 200 mg capsules AM 3 x 200 mg capsules PM
Greater than 73 | 1,200 mg/day | 3 x 200 mg capsules AM 3 x 200 mg capsules PM
* Ribavirin Oral Solution may be used in any patient regardless of body weight.

2.3 Ribavirin capsules/INTRON A Combination Therapy

Adults

Duration of Treatment – Interferon Alpha-naïve Patients
The recommended dose of ribavirin capsules when used in combination with INTRON A depends on the patient’s body weight (see Table 3). Refer to Intron A labeling for interferon dosing information. The recommended duration of treatment for patients previously untreated with interferon is 24 to 48 weeks. The duration of treatment should be individualized to the patient depending on baseline disease characteristics, response to therapy, and tolerability of the regimen [see Indications and Usage (1.1), Adverse Reactions (6.1), and Clinical Studies (14)]. After 24 weeks of treatment, virologic response should be assessed. Treatment discontinuation should be considered in any patient who has not achieved an HCV-RNA below the limit of detection of the assay by 24 weeks. There are no safety and efficacy data for treatment duration lasting longer than 48 weeks in the previously untreated patient population.

Duration of Treatment – Re-treatment with INTRON A/Ribavirin capsules in Relapse Patients
In patients who relapse following nonpegylated interferon monotherapy, the recommended duration of treatment is 24 weeks.

Table 3: Recommended Ribavirin capsules Dosing in Combination with INTRON A
Body Weight | Ribavirin Capsules
At least 75 kg | 2 x 200 mg capsules AM 3 x 200 mg capsules PM daily orally
Greater than 75 kg | 3 x 200 mg capsules AM 3 x 200 mg capsules PM daily orally

Pediatrics The recommended dose of ribavirin when used in combination with INTRON A is 15 mg/kg per day orally in two divided doses (see Table 2). Refer to Intron A labeling for interferon dosing information.

The recommended duration of treatment is 48 weeks for pediatric patients with genotype 1. After 24 weeks of treatment, virologic response should be assessed. Treatment discontinuation should be considered in any patient who has not achieved an HCV-RNA below the limit of detection of the assay by this time. The recommended duration of treatment for pediatric patients with genotype 2 and 3 is 24 weeks.

2.4 Testing Prior to Initiation of Ribavirin capsules

The following laboratory tests are recommended in all patients treated with ribavirin capsules prior to initiation of treatment and periodically thereafter.

- Standard hematologic tests - including hemoglobin (pretreatment, Week 2 and Week 4 of therapy, and as clinically appropriate [see Warnings and Precautions (5.2, 5.6)], complete and differential white blood cell counts, and platelet count.
- Blood chemistries - liver function tests and TSH.
- Pregnancy - in women of childbearing potential.
- ECG [see Warnings and Precautions (5.2)].

2.5 Dose Modifications

If severe adverse reactions or laboratory abnormalities develop during ribavirin capsules combination therapy, modify or discontinue the dose until the adverse reaction abates or decreases in severity (see Table 4) [see Warnings and Precautions (5)]. If intolerance persists after dose adjustment, combination therapy should be discontinued. Refer to PegIntron labeling for additional information regarding dose reduction of PegIntron.

Dose reduction in pediatric patients is accomplished by modifying the recommended ribavirin capsules dose from the original starting dose of 15 mg/kg daily in a two-step process to 12 mg/kg/day, then to 8 mg/kg/day, if needed (see Table 4).

Ribavirin capsules are contraindicated in patients with creatinine clearance less than 50 mL/min [see Contraindications (4)]. Patients with impaired renal function and those over the age of 50 should be carefully monitored with respect to development of anemia [see Warnings and Precautions (5.2), Use in Specific Populations (8.5), and Clinical Pharmacology (12.3)].

Ribavirin capsules should be administered with caution to patients with pre-existing cardiac disease. Assess cardiovascular status before initiation of treatment and during therapy. If there is any deterioration of cardiovascular status, discontinue combination therapy [see Warnings and Precautions (5.2)].

In patients with a history of stable cardiovascular disease, a permanent dose reduction is required if the hemoglobin decreases by 2 g/dL or more during any 4-week period. If the hemoglobin level remains below 12 g/dL after 4 weeks on a reduced dose, discontinue combination therapy.

Modify or discontinue ribavirin capsules dosing in any patient whose hemoglobin level falls below 10 g/dL (see Table 4) [see Warnings and Precautions (5.2)].

Table 4: Guidelines for Dose Modification and Discontinuation of Ribavirin capsules in combination with PegIntron or INTRON A Based on Laboratory Parameters in Adults and Pediatrics
Laboratory Parameters | Reduce Ribavirin capsules Daily Dose (see note 1) if: | Reduce PegIntron or INTRON A Dose (see note 2) if: | Discontinue Therapy if:
WBC | N/A | 1.0 to <1.5 x 10^9/L | <1.0 x 10^9/L
Neutrophils | N/A | 0.5 to <0.75 x 10^9/L | <0.5 x 10^9/L
Platelets | N/A | 25 to < 50 x 10^9/L (adults) | <25 x 10^9/L (adults)
Platelets | N/A | 50 to <70 x 10^9/L (pediatrics) | <50 x 10^9/L (pediatrics)
Creatinine | N/A | N/A | >2 mg/dL (pediatrics)
Hemoglobin in patients without history of cardiac disease | 8.5 to <10 g/dL | N/A | <8.5 g/dL
 | Reduce Ribavirin capsules Dose by 200 mg/day and PegIntron or INTRON A Dose by Half if:
Hemoglobin in patients with history of stable cardiac disease*† | ≥2 g/dL decrease in hemoglobin during any four-week period during treatment |  | <8.5 g/dL or <12 g/dL after four weeks of dose reduction
Note 1: Adult patients: 1st dose reduction of ribavirin is by 200 mg/day (except in patients receiving the 1,400 mg, dose reduction should be by 400 mg/day). If needed, 2nd dose reduction of ribavirin is by an additional 200 mg/day. Patients whose dose of ribavirin is reduced to 600 mg daily receive one 200 mg capsule in the morning and two 200 mg capsules in the evening.
Pediatric patients: 1st dose reduction of ribavirin is to 12 mg/kg/day, 2nd dose reduction of ribavirin is to 8 mg/kg/day.
Note 2: Adult patients treated with ribavirin capsules and PegIntron: 1st dose reduction of PegIntron is to 1 mcg/kg/week. If needed, 2nd dose reduction of PegIntron is to 0.5 mcg/kg/week.
Pediatric patients treated with ribavirin capsules and PegIntron: 1st dose reduction of PegIntron is to 40 mcg/m^2/week, 2nd dose reduction of PegIntron is to 20 mcg/m^2/week.
For patients on ribavirin capsules/INTRON A combination therapy: reduce INTRON A dose by 50%.
* Pediatric patients who have pre-existing cardiac conditions and experience a hemoglobin decrease greater than or equal to 2 g/dL during any 4-week period during treatment should have weekly evaluations and hematology testing.
† These guidelines are for patients with stable cardiac disease. Patients with a history of significant or unstable cardiac disease should not be treated with PegIntron/ribavirin capsules combination therapy [see Warnings and Precautions (5.2)].

Refer to labeling for INTRON A or PegIntron for additional information about how to reduce an INTRON A or PegIntron dose.

2.6 Discontinuation of Dosing

Adults In HCV genotype 1, interferon-alfa-naïve patients receiving PegIntron in combination with ribavirin, discontinue therapy if there is not at least a 2 log10 drop or loss of HCV-RNA at 12 weeks of therapy, or if HCV-RNA levels remain detectable after 24 weeks of therapy. Regardless of genotype, previously treated patients who have detectable HCV-RNA at Week 12 or 24 are highly unlikely to achieve SVR and discontinuation of therapy should be considered.

Pediatrics (3 to 17 years of age) In patients receiving PegIntron/ribavirin capsules combination (excluding HCV Genotype 2 and 3), discontinue therapy at 12 weeks if HCV-RNA has dropped less than 2 log10 compared to pretreatment level, or at 24 weeks if HCV-RNA is still detectable.

3 DOSAGE FORMS AND STRENGTHS

Ribavirin Capsules USP, 200 mg are white/white, size ‘1’ hard gelatin capsule filled with white to off-white granular powder and imprinted with ‘E’ on white cap and ‘81’ on white body with black ink.

4 CONTRAINDICATIONS

Ribavirin capsules combination therapy is contraindicated in:

- pregnancy. Ribavirin capsules may cause fetal harm when administered to a pregnant woman. Ribavirin capsules are contraindicated in women who are pregnant or planning to become pregnant. If a patient becomes pregnant while taking ribavirin capsules, the patient should be apprised of the potential hazard to the fetus [see Warnings and Precautions (5.1), and Use in Specific Populations (8.1, 8.3)].
- men whose female partners are pregnant [see Use in Specific Populations (8.3)]
- patients with known hypersensitivity reactions such as Stevens-Johnson syndrome, toxic, epidermal necrolysis, and erythema multiforme to ribavirin or any component of the product
- patients with autoimmune hepatitis
- patients with hemoglobinopathies (e.g., thalassemia major, sickle-cell anemia)
- patients with creatinine clearance less than 50 mL/min [see Clinical Pharmacology (12.3)]
- when coadministered with didanosine because exposure to the active metabolite of didanosine (dideoxyadenosine 5’-triphosphate) is increased. Fatal hepatic failure, as well as peripheral neuropathy, pancreatitis, and symptomatic hyperlactatemia/lactic acidosis, has been reported in patients receiving didanosine in combination with ribavirin [see Drug Interactions (7.1)].

5 WARNINGS AND PRECAUTIONS

5.1 Embryo-Fetal Toxicity

Ribavirin capsules may cause birth defects, miscarriage or stillbirth. Ribavirin therapy should not be started until a report of a negative pregnancy test has been obtained immediately prior to planned initiation of therapy. Female patients should use effective contraception and have periodic monitoring with pregnancy tests during treatment and during the 9-month period after treatment has been stopped. Male patients and their female partners should use effective contraception during treatment and during the 6-month period after treatment has been stopped. Extreme care must be taken to avoid pregnancy in female patients and in female partners of male patients. Ribavirin has demonstrated significant teratogenic and embryocidal effects in all animal species tested. These effects occurred at doses as low as one twentieth of the recommended human dose of ribavirin. [see Boxed Warning, Contraindications (4), and Use in Specific Populations (8.1, 8.3)].

5.2 Anemia

Hemolytic anemia was observed in approximately 10% of ribavirin/INTRON A-treated subjects in clinical trials. The anemia associated with ribavirin occurs within 1 to 2 weeks of initiation of therapy. Because the initial drop in hemoglobin may be significant, obtain hemoglobin or hematocrit levels before the start of treatment and at Week 2 and Week 4 of therapy, or more frequently if clinically indicated. Patients should then be followed as clinically appropriate [see Dosage and Administration (2.5, 2.6)].

Fatal and nonfatal myocardial infarctions have been reported in patients with anemia caused by ribavirin. Patients should be assessed for underlying cardiac disease before initiation of ribavirin therapy. Patients with pre-existing cardiac disease should have electrocardiograms administered before treatment and should be appropriately monitored during therapy. If there is any deterioration of cardiovascular status, therapy should be suspended or discontinued [see Dosage and Administration (2.5, 2.6)]. Because cardiac disease may be worsened by drug-induced anemia, patients with a history of significant or unstable cardiac disease should not use ribavirin.

5.3 Pancreatitis

Suspend ribavirin and INTRON A or PegIntron combination therapy in patients with signs and symptoms of pancreatitis and discontinue in patients with confirmed pancreatitis.

5.4 Pulmonary Disorders

Pulmonary symptoms, including dyspnea, pulmonary infiltrates, pneumonitis, pulmonary hypertension, and pneumonia, have been reported during ribavirin with alpha interferon combination therapy; occasional cases of fatal pneumonia have occurred. In addition, sarcoidosis or the exacerbation of sarcoidosis has been reported. If there is evidence of pulmonary infiltrates or pulmonary function impairment, closely monitor the patient, and if appropriate, discontinue combination therapy.

5.5 Ophthalmologic Disorders

Ribavirin is used in combination therapy with INTRON A or PegIntron. Refer to labeling for PegIntron for additional information.

5.6 Laboratory Tests

PegIntron in combination with ribavirin may cause severe decreases in neutrophil and platelet counts, and hematologic, endocrine (e.g., TSH), and hepatic abnormalities.

Obtain hematology and blood chemistry testing in patients on PegIntron/ribavirin combination therapy before the start of treatment and then periodically thereafter. In the adult clinical trial, complete blood counts (including hemoglobin, neutrophil, and platelet counts) and chemistries (including AST, ALT, bilirubin, and uric acid) were measured during the treatment period at Weeks 2, 4, 8, 12, and then at 6-week intervals, or more frequently if abnormalities developed. In pediatric subjects, the same laboratory parameters were evaluated with additional assessment of hemoglobin at treatment Week 6. TSH levels were measured every 12 weeks during the treatment period. HCV-RNA should be measured periodically during treatment [see Dosage and Administration (2)].

5.7 Dental and Periodontal Disorders

Dental and periodontal disorders have been reported in patients receiving ribavirin and interferon or peginterferon combination therapy. In addition, dry mouth could have a damaging effect on teeth and mucous membranes of the mouth during long-term treatment with the combination of ribavirin and pegylated or nonpegylated interferon alfa-2b. Advise patients to brush their teeth thoroughly twice daily and have regular dental examinations. If vomiting occurs, advise patients to rinse out their mouth thoroughly afterwards.

5.8 Concomitant Administration of Azathioprine

Pancytopenia (marked decreases in red blood cells, neutrophils, and platelets) and bone marrow suppression have been reported in the literature to occur within 3 to 7 weeks after the concomitant administration of pegylated interferon/ribavirin and azathioprine. In this limited number of patients (n=8), myelotoxicity was reversible within 4 to 6 weeks upon withdrawal of both HCV antiviral therapy and concomitant azathioprine and did not recur upon reintroduction of either treatment alone. Discontinue PegIntron, ribavirin, and azathioprine for pancytopenia, and do not reintroduce pegylated interferon/ribavirin with concomitant azathioprine [see Drug Interactions (7.4)].

5.9 Impact on Growth in Pediatric Patients

Data on the effects of PegIntron and ribavirin on growth come from an open-label study in subjects 3 through 17 years of age, in which weight and height changes were compared to U.S. normative population data. In general, the weight and height gain of pediatric subjects treated with PegIntron and ribavirin lagged behind that predicted by normative population data for the entire length of treatment. Severely inhibited growth velocity (less than 3rd percentile) was observed in 70% of the subjects while on treatment. Following treatment, rebound growth and weight gain occurred in most subjects. Long-term follow-up data in pediatric subjects, however, indicates that PegIntron in combination therapy with ribavirin may induce a growth inhibition that results in reduced adult height in some patients [see Adverse Reactions (6.1)].

Similarly, an impact on growth was seen in subjects after treatment with ribavirin and INTRON A combination therapy for one year. In a long-term follow-up trial of a limited number of these subjects, combination therapy resulted in reduced final adult height in some subjects [see Adverse Reactions (6.1)].

5.10 Not Recommended for Monotherapy and Risks Associated with Combination Therapy

Based on results of clinical trials, ribavirin monotherapy is not effective for the treatment of chronic hepatitis C virus infection; therefore, ribavirin capsules must not be used alone. The safety and efficacy of ribavirin capsules have only been established when used together with INTRON A or PegIntron (not other interferons) as combination therapy.

The safety and efficacy of ribavirin with INTRON A or PegIntron combination therapy for the treatment of HIV infection, adenovirus, RSV, parainfluenza, or influenza infections have not been established. Ribavirin capsules should not be used for these indications.

There are significant adverse reactions caused by ribavirin/INTRON A or PegIntron combination therapy, including severe depression and suicidal or homicidal ideation, hemolytic anemia, suppression of bone marrow function, autoimmune and infectious disorders, pulmonary dysfunction, pancreatitis, and diabetes. Suicidal ideation or attempts occurred more frequently among pediatric patients, primarily adolescents, compared to adult patients (2.4% versus 1%) during treatment and off-therapy follow-up. Labeling for INTRON A and PegIntron should be reviewed in their entirety for additional safety information prior to initiation of combination treatment.

6 ADVERSE REACTIONS

The following serious adverse drug reactions are discussed in other sections of the labeling:

- Embryo-Fetal Toxicity [see Warnings and Precautions (5.1)]
- Anemia [see Warnings and Precautions (5.2)]
- Pancreatitis [see Warnings and Precautions (5.3)]
- Pulmonary Disorders [see Warnings and Precautions (5.4)]
- Ophthalmic Disorders [see Warnings and Precautions (5.5)]
- Dental and Periodontal Disorders [see Warnings and Precautions (5.7)]
- Impact on Growth in Pediatric Patients [see Warnings and Precautions (5.9)]

6.1 Clinical Trials Experience

Because clinical trials are conducted under widely varying conditions, adverse reaction rates observed in the clinical trials of a drug cannot be directly compared to rates in the clinical trials of another drug and may not reflect the rates observed in clinical practice.

Clinical trials with ribavirin in combination with PegIntron or INTRON A have been conducted in over 7,800 subjects from 3 to 76 years of age.

The primary toxicity of ribavirin is hemolytic anemia. Reductions in hemoglobin levels occurred within the first 1 to 2 weeks of oral therapy. Cardiac and pulmonary reactions associated with anemia occurred in approximately 10% of patients [see Warnings and Precautions (5.2)].

Greater than 96% of all subjects in clinical trials experienced one or more adverse reactions. The most commonly reported adverse reactions in adult subjects receiving PegIntron or INTRON A in combination with ribavirin were injection site inflammation/reaction, fatigue/asthenia, headache, rigors, fevers, nausea, myalgia and anxiety/emotional lability/irritability. The most common adverse reactions in pediatric subjects, ages 3 and older, receiving ribavirin in combination with PegIntron or INTRON A were pyrexia, headache, neutropenia, fatigue, anorexia, injection site erythema, and vomiting.

The Adverse Reactions section references the following clinical trials:

- Ribavirin/PegIntron Combination therapy trials:
  - Clinical Study 1 – evaluated PegIntron monotherapy (not further described in this label; see labeling for PegIntron for information about this trial).
  - Study 2 – evaluated ribavirin 800 mg/day flat dose in combination with 1.5 mcg/kg/week PegIntron or with INTRON A.
  - Study 3 – evaluated PegIntron/weight-based ribavirin in combination with PegIntron/flat dose ribavirin regimen.
  - Study 4 – compared two PegIntron (1.5 mcg/kg/week and 1 mcg/kg/week) doses in combination with ribavirin and a third treatment group receiving Pegasys® (180 mcg/week)/Copegus® (1000 to 1200 mg/day).
  - Study 5 – evaluated PegIntron (1.5 mcg/kg/week) in combination with weight-based ribavirin in prior treatment failure subjects.
- PegIntron/Ribavirin Combination Therapy in Pediatric Patients
- Ribavirin/INTRON A Combination Therapy trials for adults and pediatrics

Serious adverse reactions have occurred in approximately 12% of subjects in clinical trials with PegIntron with or without ribavirin [see Boxed Warning, Warnings and Precautions (5)]. The most common serious events occurring in subjects treated with PegIntron and ribavirin were depression and suicidal ideation [see Warnings and Precautions (5.10)], each occurring at a frequency of less than 1%. Suicidal ideation or attempts occurred more frequently among pediatric patients, primarily adolescents, compared to adult patients (2.4% versus 1%) during treatment and off-therapy follow-up [see Warnings and Precautions (5.10)]. The most common fatal reaction occurring in subjects treated with PegIntron and ribavirin was cardiac arrest, suicidal ideation, and suicide attempt [see Warnings and Precautions (5.10)], all occurring in less than 1% of subjects.

Adverse Reaction - Ribavirin/PegIntron Combination Therapy

Adult Subjects

Adverse reactions that occurred in the clinical trial at greater than 5% incidence are provided by treatment group from the ribavirin/PegIntron Combination Therapy (Study 2) in Table 5.

Table 5: Adverse Reactions Occurring in Greater Than 5% of Adult Subjects
Adverse Reactions | Percentage of Subjects Reporting Adverse Reactions* |  | Adverse Reactions | Percentage of Subjects Reporting Adverse Reactions*
Adverse Reactions | PegIntron 1.5 mcg/kg/Ribavirin (N=511) | INTRON A/Ribavirin (N=505) | Adverse Reactions | PegIntron 1.5 mcg/kg/Ribavirin (N=511) | INTRON A/Ribavirin (N=505)
Application Site |  |  | Musculoskeletal
Injection Site Inflammation Injection Site Reaction | 25 58 | 18 36 | Myalgia | 56 | 50
Injection Site Inflammation Injection Site Reaction | 25 58 | 18 36 | Arthralgia | 34 | 28
Autonomic Nervous System |  |  | Musculoskeletal Pain | 21 | 19
Dry Mouth | 12 | 8 | Psychiatric
Increased Sweating | 11 | 7 | Insomnia | 40 | 41
Flushing | 4 | 3 | Depression | 31 | 34
Body as a Whole |  |  | Anxiety/Emotional Lability/Irritability | 47 | 47
Fatigue/Asthenia | 66 | 63 | Concentration Impaired | 17 | 21
Headache | 62 | 58 | Agitation | 8 | 5
Rigors | 48 | 41 | Nervousness | 6 | 6
Fever | 46 | 33 | Reproductive, Female
Weight Loss | 29 | 20 | Menstrual Disorder | 7 | 6
Right Upper Quadrant Pain | 12 | 6 | Resistance Mechanism
Chest Pain | 8 | 7 | Viral Infection | 12 | 12
Malaise | 4 | 6 | Fungal Infection | 6 | 1
Central/Peripheral Nervous System |  |  | Respiratory System
Dizziness | 21 | 17 | Dyspnea | 26 | 24
Endocrine |  |  | Coughing | 23 | 16
Hypothyroidism | 5 | 4 | Pharyngitis | 12 | 13
Gastrointestinal |  |  | Rhinitis | 8 | 6
Nausea | 43 | 33 | Sinusitis | 6 | 5
Anorexia | 32 | 27 | Skin and Appendages
Diarrhea | 22 | 17 | Alopecia | 36 | 32
Vomiting | 14 | 12 | Pruritus | 29 | 28
Abdominal Pain | 13 | 13 | Rash | 24 | 23
Dyspepsia | 9 | 8 | Skin Dry | 24 | 23
Constipation | 5 | 5 | Special Senses, Other
Hematologic Disorders |  |  | Taste Perversion | 9 | 4
Neutropenia | 26 | 14 | Vision Disorders
Anemia | 12 | 17 | Vision Blurred | 5 | 6
Leukopenia | 6 | 5 | Conjunctivitis | 4 | 5
Thrombocytopenia | 5 | 2
Liver and Biliary System
Hepatomegaly | 4 | 4
* A subject may have reported more than one adverse reaction within a body system/organ class category.

Table 6 summarizes the treatment-related adverse reactions in Study 4 that occurred at a greater than or equal to 10% incidence.

Table 6: Treatment-Related Adverse Reactions (Greater Than or Equal to 10% Incidence) By Descending Frequency
 | Study 4 Percentage of Subjects Reporting Treatment-Related Adverse Reactions
Adverse Reactions | PegIntron 1.5 mcg/kg with Ribavirin (N=1019) | PegIntron 1 mcg/kg with Ribavirin (N=1016) | Pegasys 180 mcg with Copegus (N=1035)
Fatigue | 67 | 68 | 64
Headache | 50 | 47 | 41
Nausea | 40 | 35 | 34
Chills | 39 | 36 | 23
Insomnia | 38 | 37 | 41
Anemia | 35 | 30 | 34
Pyrexia | 35 | 32 | 21
Injection Site Reactions | 34 | 35 | 23
Anorexia | 29 | 25 | 21
Rash | 29 | 25 | 34
Myalgia | 27 | 26 | 22
Neutropenia | 26 | 19 | 31
Irritability | 25 | 25 | 25
Depression | 25 | 19 | 20
Alopecia | 23 | 20 | 17
Dyspnea | 21 | 20 | 22
Arthralgia | 21 | 22 | 22
Pruritus | 18 | 15 | 19
Influenza-like Illness | 16 | 15 | 15
Dizziness | 16 | 14 | 13
Diarrhea | 15 | 16 | 14
Cough | 15 | 16 | 17
Weight Decreased | 13 | 10 | 10
Vomiting | 12 | 10 | 9
Unspecified Pain | 12 | 13 | 9
Dry Skin | 11 | 11 | 12
Anxiety | 11 | 11 | 10
Abdominal Pain | 10 | 10 | 10
Leukopenia | 9 | 7 | 10

The incidence of serious adverse reactions was comparable in all trials. In Study 2, the incidence of serious adverse reactions was 17% in the PegIntron/ribavirin groups compared to 14% in the INTRON A/ribavirin group. In Study 3, there was a similar incidence of serious adverse reactions reported for the weight-based ribavirin group (12%) and for the flat-dose ribavirin regimen.

In many but not all cases, adverse reactions resolved after dose reduction or discontinuation of therapy. Some subjects experienced ongoing or new serious adverse reactions during the 6-month follow-up period. In Study 2, many subjects continued to experience adverse reactions several months after discontinuation of therapy. By the end of the 6-month follow-up period, the incidence of ongoing adverse reactions by body class in the PegIntron 1.5/ribavirin group was 33% (psychiatric), 20% (musculoskeletal), and 10% (for endocrine and for GI). In approximately 10 to 15% of subjects, weight loss, fatigue, and headache had not resolved.

There have been 28 subject deaths that occurred during treatment or follow-up in Studies 2, 3, and 4. In Study 2, there was 1 suicide in a subject receiving PegIntron/ribavirin combination therapy; and 1 subject death in the INTRON A/ribavirin group (motor vehicle accident). In Study 3, there were 14 deaths, 2 of which were probable suicides and 1 was an unexplained death in a person with a relevant medical history of depression. In Study 4, there were 12 deaths, 6 of which occurred in subjects who received PegIntron/ribavirin combination therapy, 5 in the PegIntron 1.5 mcg/ribavirin arm (N=1019) and 1 in the PegIntron 1 mcg/ribavirin arm (N=1016), and 6 of which occurred in subjects receiving Pegasys/Copegus (N=1035); there were 3 suicides that occurred during the off treatment follow-up period in subjects who received PegIntron (1.5 mcg/kg)/ribavirin combination therapy.

In Studies 1 and 2, 10 to 14% of subjects receiving PegIntron, alone or in combination with ribavirin, discontinued therapy compared with 6% treated with INTRON A alone and 13% treated with INTRON A in combination with ribavirin. In Study 3, 15% of subjects receiving PegIntron in combination with weight-based ribavirin and 14% of subjects receiving PegIntron with flat-dose ribavirin discontinued therapy due to an adverse reaction. The most common reasons for discontinuation were related to known interferon effects of psychiatric, systemic (e.g., fatigue, headache), or gastrointestinal adverse reactions. In Study 4, 13% of subjects in the PegIntron 1.5 mcg/ribavirin arm, 10% in the PegIntron 1 mcg/ribavirin arm, and 13% in the Pegasys 180 mcg/Copegus arm discontinued due to adverse events.

In Study 2, dose reductions for ribavirin were similar across all three groups [see Clinical Studies (14.1)], 33 to 35%. The most common reasons for dose modifications were neutropenia (18%), or anemia (9%) (see Laboratory Values). Other common reasons included depression, fatigue, nausea, and thrombocytopenia. In Study 3, dose modifications due to adverse reactions occurred more frequently with weight-based ribavirin dosing compared to flat dosing (29% and 23%, respectively). In Study 4, 16% of subjects had a dose reduction of PegIntron to 1 mcg/kg in combination with ribavirin, with an additional 4% requiring the second dose reduction of PegIntron to 0.5 mcg/kg due to adverse events compared to 15% of subjects in the Pegasys/Copegus arm, who required a dose reduction to 135 mcg/week with Pegasys, with an additional 7% in the Pegasys/Copegus arm requiring a second dose reduction to 90 mcg/week with Pegasys.

In the PegIntron/ribavirin combination trials the most common adverse reactions were psychiatric, which occurred among 77% of subjects in Study 2 and 68% to 69% of subjects in Study 3. These psychiatric adverse reactions included most commonly depression, irritability, and insomnia, each reported by approximately 30% to 40% of subjects in all treatment groups. Suicidal behavior (ideation, attempts, and suicides) occurred in 2% of all subjects during treatment or during follow-up after treatment cessation [see Warnings and Precautions (5)]. In Study 4, psychiatric adverse reactions occurred in 58% of subjects in the PegIntron 1.5 mcg/ribavirin arm, 55% of subjects in the PegIntron 1 mcg/ribavirin arm, and 57% of subjects in the Pegasys 180 mcg/Copegus arm.

In Study 2, PegIntron/ribavirin combination therapy induced fatigue or headache in approximately two-thirds of subjects, with fever or rigors in approximately half of the subjects. The severity of some of these systemic symptoms (e.g., fever and headache) tended to decrease as treatment continued.

Subjects receiving ribavirin/PegIntron as re-treatment after failing a previous interferon combination regimen reported adverse reactions similar to those previously associated with this regimen during clinical trials of treatment-naïve subjects.

Pediatric Subjects

In general, the adverse reaction profile in the pediatric population was similar to that observed in adults. In the pediatric trial, the most prevalent adverse reactions were pyrexia (80%), headache (62%), neutropenia (33%), fatigue (30%), anorexia (29%), injection-site erythema (29%) and vomiting (27%). The majority of adverse reactions were mild or moderate in severity. Severe adverse reactions were reported in 7% (8/107) of all subjects and included injection site pain (1%), pain in extremity (1%), headache (1%), neutropenia (1%), and pyrexia (4%). Important adverse reactions that occurred in this subject population were nervousness (7%; 7/107), aggression (3%; 3/107), anger (2%; 2/107), and depression (1%; 1/107). Five subjects received levothyroxine treatment, three with clinical hypothyroidism and two with asymptomatic TSH elevations. Weight and height gain of pediatric subjects treated with PegIntron plus ribavirin lagged behind that predicted by normative population data for the entire length of treatment. Severely inhibited growth velocity (less than 3rd percentile) was observed in 70% of the subjects while on treatment.

Dose modifications of PegIntron and/or ribavirin were required in 25% of subjects due to treatment-related adverse reactions, most commonly for anemia, neutropenia and weight loss. Two subjects (2%; 2/107) discontinued therapy as the result of an adverse reaction.

Adverse reactions that occurred with a greater than or equal to 10% incidence in the pediatric trial subjects are provided in Table 7.

Table 7: Percentage of Pediatric Subjects with Treatment-Related Adverse Reactions (in At Least 10% of All Subjects)
System Organ Class Preferred Term | All Subjects (N=107)
Blood and Lymphatic System Disorders
Neutropenia | 33%
Anemia | 11%
Leukopenia | 10%
Gastrointestinal Disorders
Abdominal Pain | 21%
Abdominal Pain Upper | 12%
Vomiting | 27%
Nausea | 18%
General Disorders and Administration Site Conditions
Pyrexia | 80%
Fatigue | 30%
Injection-site Erythema | 29%
Chills | 21%
Asthenia | 15%
Irritability | 14%
Investigations
Weight Loss | 19%
Metabolism and Nutrition Disorders
Anorexia | 29%
Decreased Appetite | 22%
Musculoskeletal and Connective Tissue Disorders
Arthralgia | 17%
Myalgia | 17%
Nervous System Disorders
Headache | 62%
Dizziness | 14%
Skin and Subcutaneous Tissue Disorders
Alopecia | 17%

Ninety-four of 107 subjects enrolled in a 5-year follow-up trial. The long-term effects on growth were less in subjects treated for 24 weeks than in those treated for 48 weeks. Twenty-four percent of subjects (11/46) treated for 24 weeks and 40% of subjects (19/48) treated for 48 weeks had a >15 percentile height-for-age decrease from pre-treatment baseline to the end of 5-year follow-up. Eleven percent of subjects (5/46) treated for 24 weeks and 13% of subjects (6/48) treated for 48 weeks had a >30 percentile height-for-age decrease from pre-treatment baseline to the end of the 5-year follow-up. While observed across all age groups, the highest risk for reduced height at the end of long-term follow-up appeared to be initiation of combination therapy during the years of expected peak growth velocity [see Warnings and Precautions (5.9)].

Laboratory Values

Adult and Pediatric Subjects

The adverse reaction profile in Study 3, which compared PegIntron/weight-based ribavirin combination to a PegIntron/flat dose ribavirin regimen, revealed an increased rate of anemia with weight-based dosing (29% vs. 19% for weight-based vs. flat dose regimens, respectively). However, the majority of cases of anemia were mild and responded to dose reductions.

Changes in selected laboratory values during treatment in combination with ribavirin treatment are described below. Decreases in hemoglobin, leukocytes, neutrophils, and platelets may require dose reduction or permanent discontinuation from therapy [see Dosage and Administration (2.5)]. Changes in selected laboratory values during therapy are described in Table 8. Most of the changes in laboratory values in the PegIntron/ribavirin trial with pediatrics were mild or moderate.

Table 8: Selected Laboratory Abnormalities During Treatment with Ribavirin and PegIntron or Ribavirin and INTRON A in Previously Untreated Subjects
Laboratory Parameters* | Percentage of Subjects
Laboratory Parameters* | Adults (Study 2) |  | Pediatrics
Laboratory Parameters* | PegIntron/ Ribavirin (N=511) | INTRON A/ Ribavirin (N=505) | PegIntron/Ribavirin (N=107)*
Hemoglobin (g/dL)
9.5 to <11.0 | 26 | 27 | 30
8.0 to <9.5 | 3 | 3 | 2
6.5 to 7.9 | 0.2 | 0.2 | -
Leukocytes (x 10^9/L)
2.0 to 2.9 | 46 | 41 | 39
1.5 to <2.0 | 24 | 8 | 3
1.0 to 1.4 | 5 | 1 | -
Neutrophils (x 10^9/L)
1.0 to 1.5 | 33 | 37 | 35
0.75 to <1.0 | 25 | 13 | 26
0.5 to <0.75 | 18 | 7 | 13
<0.5 | 4 | 2 | 3
Platelets (x 10^9/L)
70 to 100 | 15 | 5 | 1
50 to <70 | 3 | 0.8 | -
30 to 49 | 0.2 | 0.2 | -
25 to <50 | - | - | 1
Total Bilirubin (mg/dL) |  |  | (µmole/L)
1.5 to 3.0 | 10 | 13 | -
1.26 to 2.59 x ULN† | - | - | 7
3.1 to 6.0 | 0.6 | 0.2 | -
2.6 to 5 x ULN† | - | - | -
6.1 to 12.0 | 0 | 0.2 | -
ALT (U/L)
2 x Baseline | 0.6 | 0.2 | 1
2.1 to 5 x Baseline | 3 | 1 | 5
5.1 to 10 x Baseline | 0 | 0 | 3
* The table summarizes the worst category observed within the period per subject per laboratory test. Only subjects with at least one treatment value for a given laboratory test are included.
† ULN=Upper limit of normal.

Hemoglobin. In Study 2, hemoglobin levels decreased to less than 11 g/dL in about 30% of subjects. In Study 3, 47% of subjects receiving weight-based dosing of ribavirin and 33% on flat-dose ribavirin had decreases in hemoglobin levels to less than 11 g/dL. Reductions in hemoglobin to less than 9 g/dL occurred more frequently in subjects receiving weight-based dosing compared to flat dosing (4% and 2%, respectively). In Study 2, dose modification was required in 9% and 13% of subjects in the PegIntron/ribavirin and INTRON A/ribavirin groups. In Study 4, subjects receiving PegIntron (1.5 mcg/kg)/ribavirin had decreases in hemoglobin levels to between 8.5 to less than 10 g/dL (28%) and to less than 8.5 g/dL (3%), whereas in patients receiving Pegasys 180 mcg/Copegus these decreases occurred in 26% and 4% of subjects, respectively. On average, hemoglobin levels became stable by treatment Weeks 4 to 6. The typical pattern observed was a decrease in hemoglobin levels by treatment Week 4 followed by stabilization and a plateau, which was maintained to the end of treatment [see Dosage and Administration (2.5)].

Neutrophils. In Study 2, decreases in neutrophil counts were observed in a majority of adult subjects treated with PegIntron/ribavirin (85%) and INTRON A/ribavirin (60%). Severe, potentially life-threatening neutropenia (less than 0.5 x 10^9/L) occurred in approximately 4% of subjects treated with PegIntron/ribavirin and 2% of subjects treated with INTRON A/ribavirin. Eighteen percent of subjects receiving PegIntron/ribavirin required modification of interferon dosage. Few subjects (less than 1%) required permanent discontinuation of treatment. Neutrophil counts generally returned to pre-treatment levels 4 weeks after cessation of therapy [see Dosage and Administration (2.5)].

Platelets. In Study 2, platelet counts decreased to less than 100,000/mm^3 in approximately 20% of subjects treated with PegIntron alone or with ribavirin and in 6% of adult subjects treated with INTRON A/ribavirin. Severe decreases in platelet counts (less than 50,000/mm^3) occur in less than 4% of adult subjects. In Study 2, 1% or 3% of subjects required dose modification of INTRON A or PegIntron, respectively. Platelet counts generally returned to pretreatment levels 4 weeks after the cessation of therapy [see Dosage and Administration (2.5)].

Thyroid Function. In Study 2, clinically apparent thyroid disorders occurred among subjects treated with either INTRON A or PegIntron (with or without ribavirin) at a similar incidence (5% for hypothyroidism and 3% for hyperthyroidism). Subjects developed new onset TSH abnormalities while on treatment and during the follow-up period. At the end of the follow-up period, 7% of subjects still had abnormal TSH values.

Bilirubin and Uric Acid. In Study 2, 10 to 14% of subjects developed hyperbilirubinemia and 33 to 38% developed hyperuricemia in association with hemolysis. Six subjects developed mild to moderate gout.

Adverse Reactions with Ribavirin/INTRON A Combination Therapy

Adult Subjects

In clinical trials, 19% and 6% of previously untreated and relapse subjects, respectively, discontinued therapy due to adverse reactions in the combination arms compared to 13% and 3% in the interferon-only arms. Selected treatment-related adverse reactions that occurred in the U.S. trials with incidence 5% or greater are provided by treatment group (see Table 9). In general, the selected treatment-related adverse reactions were reported with lower incidence in the international trials as compared to the U.S. trials, except for asthenia, influenza-like symptoms, nervousness, and pruritus.

Pediatric Subjects

In clinical trials of 118 pediatric subjects 3 to 16 years of age, 6% discontinued therapy due to adverse reactions. Dose modifications were required in 30% of subjects, most commonly for anemia and neutropenia. In general, the adverse-reaction profile in the pediatric population was similar to that observed in adults. Injection site disorders, fever, anorexia, vomiting, and emotional lability occurred more frequently in pediatric subjects compared to adult subjects. Conversely, pediatric subjects experienced less fatigue, dyspepsia, arthralgia, insomnia, irritability, impaired concentration, dyspnea, and pruritus compared to adult subjects. Selected treatment-related adverse reactions that occurred with incidence 5% or greater among all pediatric subjects who received the recommended dose of ribavirin/INTRON A combination therapy are provided in Table 9.

Table 9: Selected Treatment-Related Adverse Reactions: Previously Untreated and Relapse Adult Subjects and Previously Untreated Pediatric Subjects
Subjects Reporting Adverse Reactions* | Percentage of Subjects
Subjects Reporting Adverse Reactions* | U.S. Previously Untreated Study |  |  |  |  | U.S. Relapse Study |  | Pediatric Subjects
Subjects Reporting Adverse Reactions* | 24 weeks of treatment |  |  | 48 weeks of treatment |  | 24 weeks of treatment |  | 48 weeks of treatment
Subjects Reporting Adverse Reactions* | INTRON A/ Ribavirin (N=228) | INTRON A/ Placebo (N=231) | INTRON A/ Ribavirin (N=228) |  | INTRON A/ Placebo (N=225) | INTRON A/ Ribavirin (N=77) | INTRON A/ Placebo (N=76) | INTRON A/ Ribavirin (N=118)
Application Site Disorders
Injection Site Inflammation | 13 | 10 | 12 |  | 14 | 6 | 8 | 14
Injection Site Reaction | 7 | 9 | 8 |  | 9 | 5 | 3 | 19
Body as a Whole - General Disorders
Headache | 63 | 63 | 66 |  | 67 | 66 | 68 | 69
Fatigue | 68 | 62 | 70 |  | 72 | 60 | 53 | 58
Rigors | 40 | 32 | 42 |  | 39 | 43 | 37 | 25
Fever | 37 | 35 | 41 |  | 40 | 32 | 36 | 61
Influenza-like Symptoms | 14 | 18 | 18 |  | 20 | 13 | 13 | 31
Asthenia | 9 | 4 | 9 |  | 9 | 10 | 4 | 5
Chest Pain | 5 | 4 | 9 |  | 8 | 6 | 7 | 5
Central & Peripheral Nervous System Disorders
Dizziness | 17 | 15 | 23 |  | 19 | 26 | 21 | 20
Gastrointestinal System Disorders
Nausea | 38 | 35 | 46 |  | 33 | 47 | 33 | 33
Anorexia | 27 | 16 | 25 |  | 19 | 21 | 14 | 51
Dyspepsia | 14 | 6 | 16 |  | 9 | 16 | 9 | <1
Vomiting | 11 | 10 | 9 |  | 13 | 12 | 8 | 42
Musculoskeletal System Disorders
Myalgia | 61 | 57 | 64 |  | 63 | 61 | 58 | 32
Arthralgia | 30 | 27 | 33 |  | 36 | 29 | 29 | 15
Musculoskeletal Pain | 20 | 26 | 28 |  | 32 | 22 | 28 | 21
Psychiatric Disorders
Insomnia | 39 | 27 | 39 |  | 30 | 26 | 25 | 14
Irritability | 23 | 19 | 32 |  | 27 | 25 | 20 | 10
Depression | 32 | 25 | 36 |  | 37 | 23 | 14 | 13
Emotional Lability | 7 | 6 | 11 |  | 8 | 12 | 8 | 16
Concentration Impaired | 11 | 14 | 14 |  | 14 | 10 | 12 | 5
Nervousness | 4 | 2 | 4 |  | 4 | 5 | 4 | 3
Respiratory System Disorders
Dyspnea | 19 | 9 | 18 |  | 10 | 17 | 12 | 5
Sinusitis | 9 | 7 | 10 |  | 14 | 12 | 7 | <1
Skin and Appendages Disorders
Alopecia | 28 | 27 | 32 |  | 28 | 27 | 26 | 23
Rash | 20 | 9 | 28 |  | 8 | 21 | 5 | 17
Pruritus | 21 | 9 | 19 |  | 8 | 13 | 4 | 12
Special Senses, Other Disorders
Taste Perversion | 7 | 4 | 8 |  | 4 | 6 | 5 | <1
* Subjects reporting one or more adverse reactions. A subject may have reported more than one adverse reaction within a body system/organ class category.

During a 48-week course of therapy there was a decrease in the rate of linear growth (mean percentile assignment decrease of 7%) and a decrease in the rate of weight gain (mean percentile assignment decrease of 9%). A general reversal of these trends was noted during the 24-week post-treatment period. Long-term data in a limited number of patients, however, suggests that combination therapy may induce a growth inhibition that results in reduced final adult height in some patients [see Warnings and Precautions (5.9)].

Laboratory Values

Changes in selected hematologic values (hemoglobin, white blood cells, neutrophils, and platelets) during therapy are described below (see Table 10).

Hemoglobin. Hemoglobin decreases among subjects receiving ribavirin therapy began at Week 1, with stabilization by Week 4. In previously untreated subjects treated for 48 weeks, the mean maximum decrease from baseline was 3.1 g/dL in the U.S. trial and 2.9 g/dL in the international trial. In relapse subjects, the mean maximum decrease from baseline was 2.8 g/dL in the U.S. trial and 2.6 g/dL in the international trial. Hemoglobin values returned to pretreatment levels within 4 to 8 weeks of cessation of therapy in most subjects.

Bilirubin and Uric Acid. Increases in both bilirubin and uric acid, associated with hemolysis, were noted in clinical trials. Most changes were moderate and reversed within 4 weeks after treatment discontinuation. This observation occurred most frequently in subjects with a previous diagnosis of Gilbert’s syndrome. This has not been associated with hepatic dysfunction or clinical morbidity.

Table 10: Selected Laboratory Abnormalities During Treatment with Ribavirin and INTRON A: Previously Untreated and Relapse Adult Subjects and Previously Untreated Pediatric Subjects
 | Percentage of Subjects
 | U.S. Previously Untreated Study |  |  |  | U.S. Relapse Study |  | Pediatric Subjects
 | 24 weeks of treatment |  | 48 weeks of treatment |  | 24 weeks of treatment |  | 48 weeks of treatment
 | INTRON A/ Ribavirin (N=228) | INTRON A/ Placebo (N=231) | INTRON A/ Ribavirin (N=228) | INTRON A/ Placebo (N=225) | INTRON A/ Ribavirin (N=77) | INTRON A/ Placebo (N=76) | INTRON A/ Ribavirin (N=118)
Hemoglobin (g/dL)
9.5 to 10.9 | 24 | 1 | 32 | 1 | 21 | 3 | 24
8.0 to 9.4 | 5 | 0 | 4 | 0 | 4 | 0 | 3
6.5 to 7.9 | 0 | 0 | 0 | 0.4 | 0 | 0 | 0
<6.5 | 0 | 0 | 0 | 0 | 0 | 0 | 0
Leukocytes (x 10^9/L)
2.0 to 2.9 | 40 | 20 | 38 | 23 | 45 | 26 | 35
1.5 to 1.9 | 4 | 1 | 9 | 2 | 5 | 3 | 8
1.0 to 1.4 | 0.9 | 0 | 2 | 0 | 0 | 0 | 0
<1.0 | 0 | 0 | 0 | 0 | 0 | 0 | 0
Neutrophils (x 10^9/L)
1.0 to 1.49 | 30 | 32 | 31 | 44 | 42 | 34 | 37
0.75 to 0.99 | 14 | 15 | 14 | 11 | 16 | 18 | 15
0.5 to 0.74 | 9 | 9 | 14 | 7 | 8 | 4 | 16
<0.5 | 11 | 8 | 11 | 5 | 5 | 8 | 3
Platelets (x 10^9/L)
70 to 99 | 9 | 11 | 11 | 14 | 6 | 12 | 0.8
50 to 69 | 2 | 3 | 2 | 3 | 0 | 5 | 2
30 to 49 | 0 | 0.4 | 0 | 0.4 | 0 | 0 | 0
<30 | 0.9 | 0 | 1 | 0.9 | 0 | 0 | 0
Total Bilirubin (mg/dL)
1.5 to 3.0 | 27 | 13 | 32 | 13 | 21 | 7 | 2
3.1 to 6.0 | 0.9 | 0.4 | 2 | 0 | 3 | 0 | 0
6.1 to 12.0 | 0 | 0 | 0.4 | 0 | 0 | 0 | 0
>12.0 | 0 | 0 | 0 | 0 | 0 | 0 | 0

6.2 Postmarketing Experiences

The following adverse reactions have been identified and reported during post approval use of ribavirin in combination with INTRON A or PegIntron. Because these reactions are reported voluntarily from a population of uncertain size, it is not always possible to reliably estimate their frequency or establish a causal relationship to drug exposure.
Blood and Lymphatic System disorders
Pure red cell aplasia, aplastic anemia
Ear and Labyrinth disorders
Hearing disorder, vertigo
Respiratory, Thoracic and Mediastinal disorders
Pulmonary hypertension
Eye disorders
Serous retinal detachment
Endocrine disorders
Diabetes

7 DRUG INTERACTIONS

7.1 Didanosine

Exposure to didanosine or its active metabolite (dideoxyadenosine 5’-triphosphate) is increased when didanosine is coadministered with ribavirin, which could cause or worsen clinical toxicities; therefore, coadministration of ribavirin capsules and didanosine is contraindicated [see Contraindications (4)]. Reports of fatal hepatic failure, as well as peripheral neuropathy, pancreatitis, and symptomatic hyperlactatemia/lactic acidosis have been reported in clinical trials.

7.2 Nucleoside Analogues

Hepatic decompensation (some fatal) has occurred in cirrhotic HIV/HCV co-infected patients receiving combination antiretroviral therapy for HIV and interferon alpha and ribavirin. Patients receiving interferon with ribavirin and nucleoside reverse transcriptase inhibitors (NRTIs) should be closely monitored for treatment-associated toxicities, especially hepatic decompensation and anemia. Discontinuation of NRTIs should be considered as medically appropriate (see labeling for individual NRTI product). Dose reduction or discontinuation of interferon, ribavirin, or both should also be considered if worsening clinical toxicities are observed, including hepatic decompensation (e.g., Child-Pugh greater than 6).

Ribavirin may antagonize the cell culture antiviral activity of stavudine and zidovudine against HIV. Ribavirin has been shown in cell culture to inhibit phosphorylation of lamivudine, stavudine, and zidovudine, which could lead to decreased antiretroviral activity. However, in a study with another pegylated interferon in combination with ribavirin, no pharmacokinetic (e.g., plasma concentrations or intracellular triphosphorylated active metabolite concentrations) or pharmacodynamic (e.g., loss of HIV/HCV virologic suppress) interaction was observed when ribavirin and lamivudine (n=18), stavudine (n=10), or zidovudine (n=6) were coadministered as part of a multidrug regimen in HIV/HCV co-infected subjects. Concomitant use of ribavirin with any of these drugs should be done with caution.

7.3 Drugs Metabolized by Cytochrome P-450

Results of in vitro studies using both human and rat liver microsome preparations indicated little or no cytochrome P-450 enzyme-mediated metabolism of ribavirin, with minimal potential for P-450 enzyme-based drug interactions.

No pharmacokinetic interactions were noted between INTRON A and ribavirin capsules in a multiple-dose pharmacokinetic study.

7.4 Azathioprine

The use of ribavirin for the treatment of chronic hepatitis C in patients receiving azathioprine has been reported to induce severe pancytopenia and may increase the risk of azathioprine-related myelotoxicity. Inosine monophosphate dehydrogenase (IMDH) is required for one of the metabolic pathways of azathioprine. Ribavirin is known to inhibit IMDH, thereby leading to accumulation of an azathioprine metabolite, 6-methylthioinosine monophosphate (6-MTITP), which is associated with myelotoxicity (neutropenia, thrombocytopenia, and anemia). Patients receiving azathioprine with ribavirin should have complete blood counts, including platelet counts, monitored weekly for the first month, twice monthly for the second and third months of treatment, then monthly or more frequently if dosage or other therapy changes are necessary [see Warnings and Precautions (5.8)].

8 USE IN SPECIFIC POPULATIONS

8.1 Pregnancy

Risk Summary

Ribavirin is contraindicated for use in pregnant women and in men whose female partners are pregnant [see Contraindications (4)]. Based on animal data, ribavirin use in pregnancy may be associated with birth defects. Data from the Ribavirin Pregnancy Registry are insufficient to identify a drug-associated risk of birth defects, miscarriage, or adverse maternal or fetal outcomes (see Data). Ribavirin is known to accumulate in intracellular components from where it is cleared very slowly. In animal studies, ribavirin exposure was shown to have teratogenic and/or embryocidal effects (see Data).

All pregnancies have a background risk of birth defect, loss, or other adverse outcomes. The estimated background risk of major birth defects and miscarriage for the indicated population is unknown. In the U.S. general population, the estimated background risk of major birth defects and miscarriage is 2 to 4% and 15 to 20%, respectively.

Data

Human Data

Available data from the Ribavirin Pregnancy Registry on 88 live births from pregnancies in women directly exposed and 98 live births from pregnancies in women indirectly exposed (by a male partner) to ribavirin during pregnancy or during the 6 months prior to pregnancy show a higher rate of birth defects (9.09% and 6.12%, respectively) compared to a background birth defect rate of 2.72% in the Metropolitan Atlanta Congenital Defects Program (MACDP) birth defects surveillance system. No pattern of birth defects can be identified from these reports. The miscarriage rate was approximately 21%. The current sample size is insufficient for reaching definitive conclusions based on statistical analysis. Trends suggesting a common etiology or relationship with ribavirin exposure were not observed. Methodologic limitations of the Ribavirin Pregnancy Registry include the use of MACDP as the external comparator group. Limitations of using an external comparator include differences in methodology and populations, as well as confounding due to the underlying disease and comorbidities.

Animal Data

Embryotoxicity/teratogenicity studies with ribavirin were conducted in rats (oral doses of 0.3, 1 and 10 mg/kg on Gestation Days 6 to 15) and rabbits (oral dose of 0.1, 0.3 and 1 mg/kg on Gestation Days 6 to 18). Ribavirin demonstrated significant embryocidal and teratogenic effects at doses well below the recommended human dose in all animal species in which adequate studies have been conducted. Malformations of the skull, palate, eye, jaw, limbs, skeleton, and gastrointestinal tract were noted. The incidence and severity of teratogenic effects increased with escalation of the drug dose. Survival of fetuses and offspring was reduced [see Contraindications (4) and Warnings and Precautions (5.1)].

8.2 Lactation

Risk Summary

There are no data on the presence of ribavirin in human milk or the effects on the breastfed infant or milk production. The developmental and health benefits of breastfeeding should be considered along with the mother’s clinical need for ribavirin and any potential adverse effects on the breastfed infant from ribavirin or from the underlying maternal condition.

8.3 Females and Males of Reproductive Potential

Ribavirin may cause fetal harm when administered to a pregnant woman [see Use in Specific Populations (8.1)].

Pregnancy Testing

Ribavirin therapy should not be started until a report of a negative pregnancy test has been obtained immediately prior to planned initiation of treatment. Patients should have periodic pregnancy tests during treatment and during the 9-month period after treatment has been stopped [see Warnings and Precautions (5.1)].

Contraception

Female patients of reproductive potential should use effective contraception during treatment and for 9 months post-therapy.

Male patients and their female partners should use effective contraception during treatment with ribavirin and for the 6-month post-therapy period [see Warnings and Precautions (5.1)].

Infertility

Based on animal data, ribavirin may impair male fertility. In animal studies, these effects were mostly reversible within a few months after drug cessation [see Nonclinical Toxicology (13.1)].

8.4 Pediatric Use

Safety and effectiveness of ribavirin in combination with PegIntron has not been established in pediatric patients below the age of 3 years. For treatment with ribavirin/INTRON A, evidence of disease progression, such as hepatic inflammation and fibrosis, as well as prognostic factors for response, HCV genotype and viral load should be considered when deciding to treat a pediatric patient. The benefits of treatment should be weighed against the observed safety findings.

Long-term follow-up data in pediatric subjects indicates that ribavirin in combination with PegIntron or with INTRON A may induce a growth inhibition that results in reduced height in some patients [see Warnings and Precautions (5.9) and Adverse Reactions (6.1)].

Suicidal ideation or attempts occurred more frequently among pediatric patients, primarily adolescents, compared to adult patients (2.4% vs. 1%) during treatment and off-therapy follow-up [see Warnings and Precautions (5.10)]. As in adult patients, pediatric patients experienced other psychiatric adverse reactions (e.g., depression, emotional lability, somnolence), anemia, and neutropenia [see Warnings and Precautions (5.2)].
Juvenile Animal Toxicity Data
In a study in which rat pups were dosed postnatally with ribavirin at doses of 10, 25, and 50 mg/kg/day, drug-related deaths occurred at 50 mg/kg (at rat pup plasma concentrations below human plasma concentrations at the human therapeutic dose) between study Days 13 and 48. Rat pups dosed from postnatal Days 7 through 63 demonstrated a minor, dose-related decrease in overall growth at all doses, which was subsequently manifested as slight decreases in body weight, crown-rump length, and bone length. These effects showed evidence of reversibility, and no histopathological effects on bone were observed. No ribavirin effects were observed regarding neurobehavioral or reproductive development.

8.5 Geriatric Use

Clinical trials of ribavirin combination therapy did not include sufficient numbers of subjects aged 65 and over to determine if they respond differently from younger subjects.

Ribavirin is known to be substantially excreted by the kidney, and the risk of toxic reactions to this drug may be greater in patients with impaired renal function. Because elderly patients often have decreased renal function, care should be taken in dose selection. Renal function should be monitored and dosage adjustments made accordingly. Ribavirin should not be used in patients with creatinine clearance less than 50 mL/min [see Contraindications (4)].

In general, ribavirin capsules should be administered to elderly patients cautiously, starting at the lower end of the dosing range, reflecting the greater frequency of decreased hepatic and cardiac function, and of concomitant disease or other drug therapy. In clinical trials, elderly subjects had a higher frequency of anemia (67%) than younger patients (28%) [see Warnings and Precautions (5.2)].

8.6 Organ Transplant Recipients

The safety and efficacy of INTRON A and PegIntron alone or in combination with ribavirin for the treatment of hepatitis C in liver or other organ transplant recipients have not been established. In a small (n=16) single-center, uncontrolled case experience, renal failure in renal allograft recipients receiving interferon alpha and ribavirin combination therapy was more frequent than expected from the center’s previous experience with renal allograft recipients not receiving combination therapy. The relationship of the renal failure to renal allograft rejection is not clear.

8.7 HIV or HBV Co-infection

The safety and efficacy of PegIntron/ribavirin and INTRON A/ribavirin for the treatment of patients with HCV co-infected with HIV or HBV have not been established.

10 OVERDOSAGE

There is limited experience with overdosage. Acute ingestion of up to 20 g of ribavirin capsules, INTRON A ingestion of up to 120 million units, and subcutaneous doses of INTRON A up to 10 times the recommended doses have been reported. Primary effects that have been observed are increased incidence and severity of the adverse reactions related to the therapeutic use of INTRON A and ribavirin. However, hepatic enzyme abnormalities, renal failure, hemorrhage, and myocardial infarction have been reported with administration of single subcutaneous doses of INTRON A that exceed dosing recommendations.

There is no specific antidote for INTRON A or ribavirin overdose, and hemodialysis and peritoneal dialysis are not effective for treatment of overdose of these agents.

11 DESCRIPTION

Ribavirin, is a synthetic nucleoside analogue (purine analogue). The chemical name of ribavirin is 1-β-D-ribofuranosyl-1H-1,2,4-triazole-3-carboxamide and has the following structural formula (see Figure 1).
Figure 1: Structural Formula
Ribavirin USP is a white, crystalline powder. It is freely soluble in water and slightly soluble in anhydrous alcohol. The molecular formula is C8H12N4O5 and the molecular weight is 244.21.

Ribavirin capsules USP consist of a white to off-white granular powder in a white, opaque, gelatin capsule. Each capsule contains 200 mg ribavirin and the inactive ingredients microcrystalline cellulose, lactose monohydrate, povidone-K 30, and magnesium stearate. The capsule shell consists of titanium dioxide, sodium lauryl sulfate, and gelatin. The capsule is printed with edible ink containing black iron oxide.

Meets USP dissolution test 2.

12 CLINICAL PHARMACOLOGY

12.1 Mechanism of Action

Ribavirin is an anti-HCV agent [see Microbiology (12.4)].

12.3 Pharmacokinetics

Single- and multiple-dose pharmacokinetic properties in adults are summarized in Table 11. Ribavirin was rapidly and extensively absorbed following oral administration. However, due to first-pass metabolism, the absolute bioavailability averaged 64% (44%). There was a linear relationship between dose and AUCtf (AUC from time zero to last measurable concentration) following single doses of 200 to 1200 mg ribavirin. The relationship between dose and Cmax was curvilinear, tending to asymptote above single doses of 400 to 600 mg.

Upon multiple oral dosing, based on AUC12hr, a 6-fold accumulation of ribavirin was observed in plasma. Following oral dosing with 600 mg twice daily, steady-state was reached by approximately 4 weeks, with mean steady-state plasma concentrations of 2200 ng/mL (37%). Upon discontinuation of dosing, the mean half-life was 298 (30%) hours, which probably reflects slow elimination from nonplasma compartments.

Effect of Antacid on Absorption of Ribavirin: Coadministration of ribavirin capsules with an antacid containing magnesium, aluminum, and simethicone resulted in a 14% decrease in mean ribavirin AUCtf. The clinical relevance of results from this single-dose study is unknown.

Table 11: Mean (% CV) Pharmacokinetic Parameters for Ribavirin When Administered Individually to Adults
Parameter | Ribavirin
Parameter | Single-Dose 600 mg Oral Solution (N=14) | Single-Dose 600 mg Capsules (N=12) | Multiple-Dose 600 mg Capsules twice daily (N=12)
Tmax (hr) | 1.00 (34) | 1.7 (46)* | 3 (60)
Cmax (ng/mL) | 872 (42) | 782 (37) | 3680 (85)
AUCtf (ng·hr/mL) | 14,098 (38) | 13,400 (48) | 228,000 (25)
T1/2 (hr) |  | 43.6 (47) | 298 (30)
Apparent Volume of Distribution (L) |  | 2825 (9)†
Apparent Clearance (L/hr) |  | 38.2 (40)
Absolute Bioavailability |  | 64% (44)‡
* N=11.
† Data obtained from a single-dose pharmacokinetic study using ^14C labeled ribavirin; N=5.
‡ N=6.

Tissue Distribution: Ribavirin transport into nonplasma compartments has been most extensively studied in red blood cells and has been identified to be primarily via an es-type equilibrative nucleoside transporter. This type of transporter is present on virtually all cell types and may account for the extensive volume of distribution. Ribavirin does not bind to plasma proteins.
Metabolism and Excretion: Ribavirin has two pathways of metabolism: (i) a reversible phosphorylation pathway in nucleated cells; and (ii) a degradative pathway involving deribosylation and amide hydrolysis to yield a triazole carboxylic acid metabolite. Ribavirin and its triazole carboxamide and triazole carboxylic acid metabolites are excreted renally. After oral administration of 600 mg of ^14C-ribavirin, approximately 61% and 12% of the radioactivity was eliminated in the urine and feces, respectively, in 336 hours. Unchanged ribavirin accounted for 17% of the administered dose.
Special Populations:
Renal Dysfunction
The pharmacokinetics of ribavirin were assessed after administration of a single oral dose (400 mg) of ribavirin to non-HCV-infected subjects with varying degrees of renal dysfunction. The mean AUCtf value was threefold greater in subjects with creatinine clearance values between 10 to 30 mL/min when compared to control subjects (creatinine clearance greater than 90 mL/min). In subjects with creatinine clearance values between 30 to 60 mL/min, AUCtf was twofold greater when compared to control subjects. The increased AUCtf appears to be due to reduction of renal and nonrenal clearance in these subjects. Phase 3 efficacy trials included subjects with creatinine clearance values greater than 50 mL/min. The multiple-dose pharmacokinetics of ribavirin cannot be accurately predicted in patients with renal dysfunction. Ribavirin is not effectively removed by hemodialysis. Patients with creatinine clearance less than 50 mL/min should not be treated with ribavirin [see Contraindications (4)].
Hepatic Dysfunction
The effect of hepatic dysfunction was assessed after a single oral dose of ribavirin (600 mg). The mean AUCtf values were not significantly different in subjects with mild, moderate, or severe hepatic dysfunction (Child-Pugh Classification A, B, or C) when compared to control subjects. However, the mean Cmax values increased with severity of hepatic dysfunction and was twofold greater in subjects with severe hepatic dysfunction when compared to control subjects.
Elderly Patients
Pharmacokinetic evaluations in elderly subjects have not been performed.
Gender
There were no clinically significant pharmacokinetic differences noted in a single-dose trial of 18 male and 18 female subjects.
Pediatric Patients
Multiple-dose pharmacokinetic properties for ribavirin capsules and INTRON A in pediatric subjects with chronic hepatitis C between 5 and 16 years of age are summarized in Table 12. The pharmacokinetics of ribavirin and INTRON A (dose-normalized) are similar in adults and pediatric subjects.
Complete pharmacokinetic characteristics of ribavirin oral solution have not been determined in pediatric subjects. Ribavirin Cmin values were similar following administration of ribavirin oral solution or ribavirin capsules during 48 weeks of therapy in pediatric subjects (3 to 16 years of age).

Table 12: Mean (% CV) Multiple-dose Pharmacokinetic Parameters for INTRON A and Ribavirin Capsules When Administered to Pediatric Subjects with Chronic Hepatitis C
Parameter | Ribavirin 15 mg/kg/day as 2 divided doses (N=17) | INTRON A 3 MIU/m^2 three times weekly (N=54)
Tmax (hr) | 1.9 (83) | 5.9 (36)
Cmax (ng/mL) | 3275 (25) | 51 (48)
AUC* | 29,774 (26) | 622 (48)
Apparent Clearance L/hr/kg | 0.27 (27) | ND†
* AUC12 (ng·hr/mL) for ribavirin; AUC0-24 (IU·hr/mL) for INTRON A.
† ND=not done.

Note: numbers in parenthesis indicate % coefficient of variation.

A clinical trial in pediatric subjects with chronic hepatitis C between 3 and 17 years of age was conducted in which pharmacokinetics for PegIntron and ribavirin (capsules and oral solution) were evaluated. In pediatric subjects receiving body surface area-adjusted dosing of PegIntron at 60 mcg/m^2/week, the log transformed ratio estimate of exposure during the dosing interval was predicted to be 58% [90% CI: 141%, 177%] higher than observed in adults receiving 1.5 mcg/kg/week. The pharmacokinetics of ribavirin (dose-normalized) in this trial were similar to those reported in a prior study of ribavirin in combination with INTRON A in pediatric subjects and in adults.

Effect of Food on Absorption of Ribavirin

Both AUCtf and Cmax increased by 70% when ribavirin capsules were administered with a high-fat meal (841 kcal, 53.8 g fat, 31.6 g protein, and 57.4 g carbohydrate) in a single-dose pharmacokinetic study [see Dosage and Administration (2)].

12.4 Microbiology

Mechanism of Action

The mechanism by which ribavirin contributes to its antiviral efficacy in the clinic is not fully understood. Ribavirin has direct antiviral activity in cell culture against many RNA viruses. Ribavirin increases the mutation frequency in the genomes of several RNA viruses and ribavirin triphosphate inhibits HCV polymerase in a biochemical reaction.

Antiviral Activity in Cell Culture

The antiviral activity of ribavirin in the HCV replicon is not well understood and has not been defined because of the cellular toxicity of ribavirin. Direct antiviral activity has been observed in cell culture of other RNA viruses. The anti-HCV activity of interferon was demonstrated in cell culture using self-replicating HCV RNA (HCV replicon cells) or HCV infection.

Resistance

HCV genotypes show wide variability in their response to pegylated recombinant human interferon/ribavirin therapy. Genetic changes associated with the variable response have not been identified.

Cross-resistance

There is no reported cross-resistance between pegylated/non-pegylated interferons and ribavirin.

13 NONCLINICAL TOXICOLOGY

13.1 Carcinogenesis, Mutagenesis, Impairment of Fertility

Carcinogenesis

Ribavirin did not cause an increase in any tumor type when administered for 6 months in the transgenic p53 deficient mouse model at doses up to 300 mg/kg (estimated human equivalent of 25 mg/kg based on body surface area adjustment for a 60 kg adult; approximately 1.9 times the maximum recommended human daily dose). Ribavirin was noncarcinogenic when administered for 2 years to rats at doses up to 40 mg/kg (estimated human equivalent of 5.71 mg/kg based on body surface area adjustment for a 60 kg adult).

Mutagenesis

Ribavirin demonstrated increased incidences of mutation and cell transformation in multiple genotoxicity assays. Ribavirin was active in the Balb/3T3 In Vitro Cell Transformation Assay. Mutagenic activity was observed in the mouse lymphoma assay, and at doses of 20 to 200 mg/kg (estimated human equivalent of 1.67 to 16.7 mg/kg, based on body surface area adjustment for a 60 kg adult; 0.1 to 1 times the maximum recommended human 24-hour dose of ribavirin) in a mouse micronucleus assay. A dominant lethal assay in rats was negative, indicating that if mutations occurred in rats they were not transmitted through male gametes.

Impairment of Fertility

In studies in mice to evaluate the time course and reversibility of ribavirin-induced testicular degeneration at doses of 15 to 150 mg/kg/day (estimated human equivalent of 1.25 to 12.5 mg/kg/day, based on body surface area adjustment for a 60-kg adult; 0.1 to 0.8 times the maximum human 24-hour dose of ribavirin) administered for 3 or 6 months, abnormalities in sperm occurred. Upon cessation of treatment, recovery from ribavirin-induced testicular toxicity was mostly apparent within 1 or 2 spermatogenesis cycles.

13.2 Animal Toxicology and Pharmacology

Long-term studies in the mouse and rat [18 to 24 months; doses of 20 to 75 and 10 to 40 mg/kg/day, respectively (estimated human equivalent doses of 1.67 to 6.25 and 1.43 to 5.71 mg/kg/day, respectively, based on body surface area adjustment for a 60 kg adult; approximately 0.1 to 0.4 times the maximum human 24-hour dose of ribavirin)] have demonstrated a relationship between chronic ribavirin exposure and increased incidences of vascular lesions (microscopic hemorrhages) in mice. In rats, retinal degeneration occurred in controls, but the incidence was increased in ribavirin-treated rats.

14 CLINICAL STUDIES

Clinical Study 1 evaluated PegIntron monotherapy. See PegIntron labeling for information about this trial.

14.1 Ribavirin/PegIntron Combination Therapy

Adult Subjects

Study 2
A randomized trial compared treatment with two PegIntron/ribavirin regimens [PegIntron 1.5 mcg/kg subcutaneously once weekly/ribavirin 800 mg orally daily (in divided doses); PegIntron 1.5 mcg/kg subcutaneously once weekly for 4 weeks then 0.5 mcg/kg subcutaneously once weekly for 44 weeks/ribavirin 1000 or 1200 mg orally daily (in divided doses)] with INTRON A [3 MIU subcutaneously three times weekly/ribavirin 1000 or 1200 mg orally daily (in divided doses)] in 1,530 adults with chronic hepatitis C. Interferon-naïve subjects were treated for 48 weeks and followed for 24 weeks post-treatment. Eligible subjects had compensated liver disease, detectable HCV-RNA, elevated ALT, and liver histopathology consistent with chronic hepatitis.

Response to treatment was defined as undetectable HCV-RNA at 24 weeks post-treatment (see Table 13). The response rate to the PegIntron 1.5 mcg/kg and ribavirin 800 mg dose was higher than the response rate to INTRON A/ribavirin (see Table 13). The response rate to PegIntron 1.5→0.5 mcg/kg/ribavirin was essentially the same as the response to INTRON A/ ribavirin (data not shown).

Table 13: Rates of Response to Combination Treatment – Study 2
 | PegIntron 1.5 mcg/kg once weekly Ribavirin 800 mg once daily | INTRON A 3 MIU three times weekly Ribavirin 1000/1200 mg once daily
Overall response*,† | 52% (264/511) | 46% (231/505)
Genotype 1 | 41% (141/348) | 33% (112/343)
Genotype 2 to 6 | 75% (123/163) | 73% (119/162)
* Serum HCV-RNA was measured with a research-based quantitative polymerase chain reaction assay by a central laboratory.
† Difference in overall treatment response (PegIntron/ribavirin vs. INTRON A/ribavirin) is 6% with 95% confidence interval of (0.18, 11.63) adjusted for viral genotype and presence of cirrhosis at baseline. Response to treatment was defined as undetectable HCV-RNA at 24 weeks post-treatment.

Subjects with viral genotype 1, regardless of viral load, had a lower response rate to PegIntron (1.5 mcg/kg)/ribavirin (800 mg) compared to subjects with other viral genotypes. Subjects with both poor prognostic factors (genotype 1 and high viral load) had a response rate of 30% (78/256) compared to a response rate of 29% (71/247) with INTRON A/ ribavirin combination therapy.

Subjects with lower body weight tended to have higher adverse-reaction rates [see Adverse Reactions (6.1)] and higher response rates than subjects with higher body weights. Differences in response rates between treatment arms did not substantially vary with body weight.

Treatment response rates with PegIntron/ribavirin combination therapy were 49% in men and 56% in women. Response rates were lower in African American and Hispanic subjects and higher in Asians compared to Caucasians. Although African Americans had a higher proportion of poor prognostic factors compared to Caucasians, the number of non-Caucasians studied (11% of the total) was insufficient to allow meaningful conclusions about differences in response rates after adjusting for prognostic factors in this trial.

Liver biopsies were obtained before and after treatment in 68% of subjects. Compared to baseline, approximately two-thirds of subjects in all treatment groups were observed to have a modest reduction in inflammation.

Study 3
In a large United States community-based trial, 4,913 subjects with chronic hepatitis C were randomized to receive PegIntron 1.5 mcg/kg subcutaneously once weekly in combination with a ribavirin dose of 800 to 1400 mg (weight-based dosing [WBD]) or 800 mg (flat) orally daily (in divided doses) for 24 or 48 weeks based on genotype. Response to treatment was defined as undetectable HCV-RNA (based on an assay with a lower limit of detection of 125 IU/mL) at 24 weeks post-treatment.

Treatment with PegIntron 1.5 mcg/kg and ribavirin 800 to 1400 mg resulted in a higher sustained virologic response compared to PegIntron in combination with a flat 800 mg daily dose of ribavirin. Subjects weighing greater than 105 kg obtained the greatest benefit with WBD, although a modest benefit was also observed in subjects weighing greater than 85 to 105 kg (see Table 14). The benefit of WBD in subjects weighing greater than 85 kg was observed with HCV genotypes 1 to 3. Insufficient data were available to reach conclusions regarding other genotypes. Use of WBD resulted in an increased incidence of anemia [see Adverse Reactions (6.1)].

Table 14: SVR Rate by Treatment and Baseline Weight - Study 3

Treatment Group | Subject Baseline Weight
Treatment Group | <65 kg (<143 lb) | 65 to 85 kg (143 to 188 lb) | >85 to 105 kg (>188 to 231 lb) | >105 kg (>231 lb)
WBD* | 50% (173/348) | 45% (449/994) | 42% (351/835) | 47% (138/292)
Flat | 51% (173/342) | 44% (443/1011) | 39% (318/819) | 33% (91/272)
* P=0.01, primary efficacy comparison (based on data from subjects weighing 65 kg or higher at baseline and utilizing a logistic regression analysis that includes treatment [WBD or Flat], genotype and presence/absence of advanced fibrosis, in the model).

A total of 1,552 subjects weighing greater than 65 kg in Study 3 had genotype 2 or 3 and were randomized to 24 or 48 weeks of therapy. No additional benefit was observed with the longer treatment duration.

Study 4
A large randomized trial compared the safety and efficacy of treatment for 48 weeks with two PegIntron/ribavirin regimens [PegIntron 1.5 mcg/kg and 1 mcg/kg subcutaneously once weekly both in combination with ribavirin 800 to 1400 mg PO daily (in two divided doses)] and Pegasys 180 mcg subcutaneously once weekly in combination with Copegus 1000 to 1200 mg PO daily (in two divided doses) in 3,070 treatment-naïve adults with chronic hepatitis C genotype 1. In this trial, lack of early virologic response (undetectable HCV-RNA or greater than or equal to 2 log10 reduction from baseline) by treatment Week 12 was the criterion for discontinuation of treatment. SVR was defined as undetectable HCV-RNA (Roche COBAS TaqMan assay, a lower limit of quantitation of 27 IU/mL) at 24 weeks post-treatment (see Table 15).

Table 15: SVR Rate by Treatment – Study 4
% (number) of Subjects
PegIntron 1.5 mcg/kg/Ribavirin | PegIntron 1 mcg/kg/Ribavirin | Pegasys 180 mcg/Copegus
40 (406/1019) | 38 (386/1016) | 41 (423/1035)

Overall SVR rates were similar among the three treatment groups. Regardless of treatment group, SVR rates were lower in subjects with poor prognostic factors. Subjects with poor prognostic factors randomized to PegIntron (1.5 mcg/kg)/ribavirin or Pegasys/Copegus, however, achieved higher SVR rates compared to similar subjects randomized to PegIntron 1 mcg/kg/ribavirin. For the PegIntron 1.5 mcg/kg and ribavirin dose, SVR rates for subjects with and without the following prognostic factors were as follows: cirrhosis (10% vs. 42%), normal ALT levels (32% vs. 42%), baseline viral load greater than 600,000 IU/mL (35% vs. 61%), 40 years of age and older (38% vs. 50%), and African American race (23% vs. 44%). In subjects with undetectable HCV-RNA at treatment Week 12 who received PegIntron (1.5 mcg/kg)/ribavirin, the SVR rate was 81% (328/407).

Study 5 - Ribavirin/PegIntron Combination Therapy in Prior Treatment Failures
In a noncomparative trial, 2,293 subjects with moderate to severe fibrosis who failed previous treatment with combination alpha interferon/ribavirin were re-treated with PegIntron, 1.5 mcg/kg subcutaneously, once weekly, in combination with weight adjusted ribavirin. Eligible subjects included prior nonresponders (subjects who were HCV-RNA positive at the end of a minimum 12 weeks of treatment) and prior relapsers (subjects who were HCV-RNA negative at the end of a minimum 12 weeks of treatment and subsequently relapsed after post-treatment follow-up). Subjects who were negative at Week 12 were treated for 48 weeks and followed for 24 weeks post-treatment. Response to treatment was defined as undetectable HCV-RNA at 24 weeks post-treatment (measured using a research-based test, limit of detection 125 IU/mL). The overall response rate was 22% (497/2293) (99% CI: 19.5, 23.9). Subjects with the following characteristics were less likely to benefit from re-treatment: previous nonresponse, previous pegylated interferon treatment, significant bridging fibrosis or cirrhosis, and genotype 1 infection.
The re-treatment sustained virologic response rates by baseline characteristics are summarized in Table 16.

Table 16: SVR Rates by Baseline Characteristics of Prior Treatment Failures - Study 5
HCV Genotype/Metavir Fibrosis Score | Overall SVR by Previous Response and Treatment
HCV Genotype/Metavir Fibrosis Score | Nonresponder |  | Relapser
HCV Genotype/Metavir Fibrosis Score | interferon alfa/ribavirin % (number of subjects) | peginterferon (2a and 2b combined)/ribavirin % (number of subjects) | interferon alfa/ribavirin % (number of subjects) | peginterferon (2a and 2b combined)/ribavirin % (number of subjects)
Overall | 18 (158/903) | 6 (30/476) | 43 (130/300) | 35 (113/344)
HCV 1 | 13 (98/761) | 4 (19/431) | 32 (67/208) | 23 (56/243)
F2 | 18 (36/202) | 6 (7/117) | 42 (33/79) | 32 (23/72)
F3 | 16 (38/233) | 4 (4/112) | 28 (16/58) | 21 (14/67)
F4 | 7 (24/325) | 4 (8/202) | 26 (18/70) | 18 (19/104)
HCV 2/3 | 49 (53/109) | 36 (10/28) | 67 (54/81) | 57 (52/92)
F2 | 68 (23/34) | 56 (5/9) | 76 (19/25) | 61 (11/18)
F3 | 39 (11/28) | 38 (3/8) | 67 (18/27) | 62 (18/29)
F4 | 40 (19/47) | 18 (2/11) | 59 (17/29) | 51 (23/45)
HCV 4 | 17 (5/29) | 7 (1/15) | 88 (7/8) | 50 (4/8)

Achievement of an undetectable HCV-RNA at treatment Week 12 was a strong predictor of SVR. In this trial, 1,470 (64%) subjects did not achieve an undetectable HCV-RNA at treatment Week 12, and were offered enrollment into long-term treatment trials, due to an inadequate treatment response. Of the 823 (36%) subjects who were HCV-RNA undetectable at treatment Week 12, those infected with genotype 1 had an SVR of 48% (245/507), with a range of responses by fibrosis scores (F4-F2) of 39 to 55%. Subjects infected with genotype 2/3 who were HCV-RNA undetectable at treatment Week 12 had an overall SVR of 70% (196/281), with a range of responses by fibrosis scores (F4-F2) of 60 to 83%. For all genotypes, higher fibrosis scores were associated with a decreased likelihood of achieving SVR.

Pediatric Subjects

Previously untreated pediatric subjects 3 to 17 years of age with compensated chronic hepatitis C and detectable HCV-RNA were treated with ribavirin 15 mg/kg per day and PegIntron 60 mcg/m^2 once weekly for 24 or 48 weeks based on HCV genotype and baseline viral load. All subjects were to be followed for 24 weeks post-treatment. A total of 107 subjects received treatment, of which 52% were female, 89% were Caucasian, and 67% were infected with HCV Genotype 1. Subjects infected with Genotypes 1, 4 or Genotype 3 with HCV-RNA greater than or equal to 600,000 IU/mL received 48 weeks of therapy while those infected with Genotype 2 or Genotype 3 with HCV-RNA less than 600,000 IU/mL received 24 weeks of therapy. The trial results are summarized in Table 17.

Table 17: Sustained Virologic Response Rates by Genotype and Assigned Treatment Duration – Pediatric Trial
Genotype | All Subjects N=107
Genotype | 24 Weeks | 48 Weeks
Genotype | Virologic Response N*,† (%) | Virologic Response N*,† (%)
All | 26/27 (96.3) | 44/80 (55.0)
1 | - | 38/72 (52.8)
2 | 14/15 (93.3) | -
3‡ | 12/12 (100) | 2/3 (66.7)
4 | - | 4/5 (80.0)
* Response to treatment was defined as undetectable HCV-RNA at 24 weeks post-treatment.
† N=number of responders/number of subjects with given genotype and assigned treatment duration.
‡ Subjects with genotype 3 low viral load (less than 600,000 IU/mL) were to receive 24 weeks of treatment while those with genotype 3 and high viral load were to receive 48 weeks of treatment.

14.2 Ribavirin/INTRON A Combination Therapy

Adult Subjects

Previously Untreated Subjects

Adults with compensated chronic hepatitis C and detectable HCV-RNA (assessed by a central laboratory using a research-based RT-PCR assay) who were previously untreated with alpha interferon therapy were enrolled into two multicenter, double-blind trials (U.S. and international) and randomized to receive ribavirin capsules 1200 mg/day (1000 mg/day for subjects weighing less than or equal to 75 kg) and INTRON A 3 MIU three times weekly or INTRON A and placebo for 24 or 48 weeks followed by 24 weeks of off-therapy follow-up. The international trial did not contain a 24-week INTRON A and placebo treatment arm. The U.S. trial enrolled 912 subjects who, at baseline, were 67% male, 89% Caucasian with a mean Knodell HAI score (I+II+III) of 7.5, and 72% genotype 1. The international trial, conducted in Europe, Israel, Canada, and Australia, enrolled 799 subjects (65% male, 95% Caucasian, mean Knodell score 6.8, and 58% genotype 1).

Trial results are summarized in Table 18.

Table 18: Virologic and Histologic Responses: Previously Untreated Subjects*
 | U.S. Trial |  |  |  | International Trial
 | 24 weeks of treatment |  | 48 weeks of treatment |  | 24 weeks of treatment | 48 weeks of treatment
 | INTRON A/Ribavirin(N=228) | INTRON A/Placebo (N=231) | INTRON A/Ribavirin (N=228) | INTRON A/Placebo (N=225) | INTRON A/Ribavirin (N=265) | INTRON A/Ribavirin (N=268) | INTRON A/Placebo (N=266)
Virologic
Response
Responder† | 65 (29) | 13 (6) | 85 (37) | 27 (12) | 86 (32) | 113 (42) | 46 (17)
Nonresponder | 147 (64) | 194 (84) | 110 (48) | 168 (75) | 158 (60) | 120 (45) | 196 (74)
Missing Data | 16 (7) | 24 (10) | 33 (14) | 30 (13) | 21 (8) | 35 (13) | 24 (9)
Histologic
Response
Improvement‡ | 102 (45) | 77 (33) | 96 (42) | 65 (29) | 103 (39) | 102 (38) | 69 (26)
No improvement | 77 (34) | 99 (43) | 61 (27) | 93 (41) | 85 (32) | 58 (22) | 111 (41)
Missing Data | 49 (21) | 55 (24) | 71 (31) | 67 (30) | 77 (29) | 108 (40) | 86 (32)
* Number (%) of subjects.
†Defined as HCV-RNA below limit of detection using a research-based RT-PCR assay at end of treatment and during follow-up period.
‡Defined as post-treatment (end of follow-up) minus pretreatment liver biopsy Knodell HAI score (I+II+III) improvement of greater than or equal to 2 points.

Of subjects who had not achieved HCV-RNA below the limit of detection of the research-based assay by Week 24 of ribavirin/INTRON A treatment, less than 5% responded to an additional 24 weeks of combination treatment.

Among subjects with HCV Genotype 1 treated with ribavirin/INTRON A therapy who achieved HCV-RNA below the detection limit of the research-based assay by 24 weeks, those randomized to 48 weeks of treatment had higher virologic responses compared to those in the 24-week treatment group. There was no observed increase in response rates for subjects with HCV non-genotype 1 randomized to ribavirin/INTRON A therapy for 48 weeks compared to 24 weeks.

Relapse Subjects

Subjects with compensated chronic hepatitis C and detectable HCV-RNA (assessed by a central laboratory using a research-based RT-PCR assay) who had relapsed following one or two courses of interferon therapy (defined as abnormal serum ALT levels) were enrolled into two multicenter, double-blind trials (U.S. and international) and randomized to receive ribavirin 1200 mg/day (1000 mg/day for subjects weighing ≤75 kg) and INTRON A 3 MIU three times weekly or INTRON A and placebo for 24 weeks followed by 24 weeks of off-therapy follow-up. The U.S. trial enrolled 153 subjects who, at baseline, were 67% male, 92% Caucasian with a mean Knodell HAI score (I+II+III) of 6.8, and 58% genotype 1. The international trial, conducted in Europe, Israel, Canada, and Australia, enrolled 192 subjects (64% male, 95% Caucasian, mean Knodell score 6.6, and 56% genotype 1). Trial results are summarized in Table 19.

Table 19: Virologic and Histologic Responses: Relapse Subjects*
 | U.S. Trial |  | International Trial
 | INTRON A/ Ribavirin (N=77) | INTRON A/ Placebo (N=76) | INTRON A/ Ribavirin (N=96) | INTRON A/ Placebo (N=96)
Virologic Response
Responder† | 33 (43) | 3 (4) | 46 (48) | 5 (5)
Nonresponder | 36 (47) | 66 (87) | 45 (47) | 91 (95)
Missing Data | 8 (10) | 7 (9) | 5 (5) | 0 (0)
Histologic Response
Improvement‡ | 38 (49) | 27 (36) | 49 (51) | 30 (31)
No improvement | 23 (30) | 37 (49) | 29 (30) | 44 (46)
Missing Data | 16 (21) | 12 (16) | 18 (19) | 22 (23)
* Number (%) of subjects.
† Defined as HCV-RNA below limit of detection using a research-based RT-PCR assay at end of treatment and during follow-up period.
‡Defined as post-treatment (end of follow-up) minus pretreatment liver biopsy Knodell HAI score (I+II+III) improvement of greater than or equal to 2 points.

Virologic and histologic responses were similar among male and female subjects in both the previously untreated and relapse trials.

Pediatric Subjects

Pediatric subjects 3 to 16 years of age with compensated chronic hepatitis C and detectable HCV-RNA (assessed by a central laboratory using a research-based RT-PCR assay) were treated with ribavirin 15 mg/kg per day and INTRON A 3 MIU/m^2 three times weekly for 48 weeks followed by 24 weeks of off-therapy follow-up. A total of 118 subjects received treatment, of which 57% were male, 80% Caucasian, and 78% genotype 1. Subjects less than 5 years of age received ribavirin oral solution and those 5 years of age or older received either ribavirin oral solution or capsules.

Trial results are summarized in Table 20.

Table 20: Virologic Response: Previously Untreated Pediatric Subjects*
 | INTRON A 3 MIU/m^2 three times weekly/Ribavirin 15 mg/kg/day
Overall Response† (N=118) | 54 (46)
Genotype 1 (N=92) | 33 (36)
Genotype non-1 (N=26) | 21 (81)
* Number (%) of subjects.
† Defined as HCV-RNA below limit of detection using a research-based RT-PCR assay at end of treatment and during follow-up period.

Subjects with viral genotype 1, regardless of viral load, had a lower response rate to INTRON A/ribavirin combination therapy compared to subjects with genotype non-1, 36% vs. 81%. Subjects with both poor prognostic factors (genotype 1 and high viral load) had a response rate of 26% (13/50).

16 HOW SUPPLIED/STORAGE AND HANDLING

Ribavirin Capsules USP, 200 mg are white/white, size ‘1’ hard gelatin capsule filled with white to off-white granular powder and imprinted with ‘E’ on white cap and ‘81’ on white body with black ink.

Bottles of 42 NDC 65862-290-42
Bottles of 56 NDC 65862-290-56
Bottles of 70 NDC 65862-290-70
Bottles of 84 NDC 65862-290-84
Bottles of 180 NDC 65862-290-18
Bottles of 500 NDC 65862-290-05

Store at 20° to 25°C (68° to 77°F); excursions permitted to 15° to 30°C (59° to 86°F) [see USP Controlled Room Temperature].

17 PATIENT COUNSELING INFORMATION

Advise the patient to read the FDA-approved patient labeling (Medication Guide).

Anemia

The most common adverse experience occurring with ribavirin capsules is anemia, which may be severe [see Warnings and Precautions (5.2) and Adverse Reactions (6)]. Advise patients that laboratory evaluations are required prior to starting therapy and periodically thereafter [see Dosage and Administration (2.4)]. Advise patients to be well hydrated, especially during the initial stages of treatment.

Embryo-Fetal Toxicity

Inform females of reproductive potential and pregnant women that ribavirin capsules may cause birth defects, miscarriage, and stillbirth. Advise females of reproductive potential that they must have a pregnancy test prior to initiating treatment and periodically during therapy. Advise female patients of reproductive potential to use effective contraception during treatment with ribavirin and for 9 months post therapy and male patients with female partners of reproductive potential to use effective contraception during treatment with ribavirin and for 6 months post therapy. Advise patients to notify the physician immediately in the event of a pregnancy [see Contraindications (4), Warnings and Precautions (5.1), and Use in Specific Populations (8.1, 8.3)].

Missed Dose

Inform patients that in the event a dose is missed, the missed dose should be taken as soon as possible during the same day. Patients should not double the next dose. Advise patients to contact their healthcare provider if they have questions.

Dental and Periodontal Disorders

Advise patients to brush their teeth thoroughly twice daily and have regular dental examinations. If vomiting occurs, advise patients to rinse out their mouth thoroughly afterwards [see Warnings and Precautions (5.7)].

The brands listed are trademarks of their respective owners and are not trademarks of Aurobindo Pharma Limited.
Dispense with Medication Guide available at: www.aurobindousa.com/medication-guides
Distributed by:
Aurobindo Pharma USA, Inc.
279 Princeton-Hightstown Road
East Windsor, NJ 08520
Manufactured by:
Aurobindo Pharma Limited
Hyderabad-500 032, India
Revised: 07/2023
Dispense with Medication Guide available at: www.aurobindousa.com/medication-guides

MEDICATION GUIDE

Ribavirin (rye” ba vye’ rin) Capsules

What is the most important information I should know about ribavirin capsules?
1. Ribavirin capsules may cause birth defects, miscarriage or death of your unborn baby. Do not take ribavirin capsules if you or your sexual partner is pregnant or plan to become pregnant.

In females: Do not become pregnant during treatment or within 9 months after you stop treatment with ribavirin capsules.

- Females must have a pregnancy test before starting ribavirin capsules, during treatment with ribavirin capsules, and for 9 months after you stop treatment with ribavirin capsules.
- You must use effective birth control during treatment and for 9 months after you stop treatment with ribavirin capsules.

In males: Your sexual partner should not become pregnant during your treatment or within 6 months after you stop treatment with ribavirin capsules. You and your female sexual partner must use effective birth control during treatment and for 6 months after you stop treatment with ribavirin capsules.

Tell your healthcare provider right away if:

- You become pregnant during treatment or within 9 months after you stop taking ribavirin capsules.
- Your female sexual partner becomes pregnant during your treatment or within 6 months after you stop treatment with ribavirin capsules.

2. Ribavirin capsules may cause a significant drop in your red blood cell count and cause anemia in some cases. Anemia has been associated with worsening of heart problems, and in rare cases can cause a heart attack and death. Tell your healthcare provider if you have ever had any heart problems. Ribavirin capsules may not be right for you. Get medical help right away if you experience chest pain.
3. Do not take ribavirin capsules alone to treat chronic hepatitis C infection. Ribavirin capsules should be used in combination with either interferon alfa-2b or peginterferon alfa-2b to treat chronic hepatitis C infection.
What are ribavirin capsules?

Ribavirin capsules are a medicine used with either interferon alfa-2b or peginterferon alfa-2b to treat chronic (lasting a long time) hepatitis C infection in people 3 years and older with liver disease.

It is not known if ribavirin capsules use for longer than 1 year is safe and will work.

It is not known if ribavirin capsules use in children younger than 3 years old is safe and will work.

Who should not take ribavirin capsules?

See “What is the most important information I should know about ribavirin capsules?”

Do not take ribavirin capsules if you have:

- ever had serious allergic reactions to the ingredients in ribavirin capsules. See the end of this Medication Guide for a complete list of ingredients.
- certain types of hepatitis (autoimmune hepatitis).
- certain blood disorders (hemoglobinopathies).
- severe kidney disease.
- taken or currently take didanosine.

Talk to your healthcare provider before taking ribavirin capsules if you have any of these conditions.

What should I tell my healthcare provider before taking ribavirin capsules?

Before you take ribavirin capsules, tell your healthcare provider if you have or ever had:

- treatment for hepatitis C that did not work for you
- breathing problems. Ribavirin capsules may cause or worsen breathing problems you already have.
- vision problems. Ribavirin capsules may cause eye problems or worsen eye problems you already have. You should have an eye exam before you start treatment with ribavirin capsules.
- certain blood disorders such as anemia (low red blood cell count)
- high blood pressure, heart problems, or have had a heart attack. Your healthcare provider should check your blood and heart before you start treatment with ribavirin capsules.
- thyroid problems
- liver problems other than hepatitis C infection
- human immunodeficiency virus (HIV) or any immunity problems
- mental health problems, including depression and thoughts of hurting yourself or others
- kidney problems
- an organ transplant
- diabetes. Ribavirin capsules may make your diabetes worse or harder to treat.
- any other medical condition
- are breastfeeding. It is not known if ribavirin passes into your breast milk. You and your healthcare provider should decide if you will take ribavirin capsules or breastfeed.

Tell your healthcare provider about all the medicines you take, including prescription medicines, vitamins, and herbal supplements. Ribavirin capsules may affect the way other medicines work.

Especially tell your healthcare provider if you take didanosine or a medicine that contains azathioprine.

Know the medicines you take. Keep a list of them to show your healthcare provider or pharmacist when you get a new medicine.

How should I take ribavirin capsules?

- Take ribavirin capsules exactly as your healthcare provider tells you. Your healthcare provider will tell you how much ribavirin capsules to take and when to take them.
- Take ribavirin capsules with food.
- Take ribavirin capsules whole. Do not open, break, or crush ribavirin capsules before swallowing. If you cannot swallow ribavirin capsules whole, tell your healthcare provider.
- If you miss a dose of ribavirin capsules, take the missed dose as soon as possible during the same day. Do not double the next dose. If you have questions about what to do, call your healthcare provider.
- If you take too much ribavirin capsules, call your healthcare provider or go to the nearest hospital emergency room right away.

What are the possible side effects of ribavirin capsules?

Ribavirin capsules may cause serious side effects, including:

See “What is the most important information I should know about ribavirin capsules?”

- Swelling and irritation of your pancreas (pancreatitis). Symptoms may include: stomach pain, nausea, vomiting, or diarrhea.
- Serious breathing problems. Difficulty breathing may be a sign of a serious lung infection (pneumonia) that can lead to death.
- Serious eye problems that may lead to vision loss or blindness.
- Dental problems. Brush your teeth well 2 times each day. Get regular dental exams. If you vomit at any time during treatment with ribavirin capsules, rinse out your mouth well.
- Severe blood disorders. You may have an increased risk of developing severe blood disorders when ribavirin capsules is used in combination with pegylated alpha interferons and azathioprine. Your healthcare provider should do blood tests during your treatment with ribavirin capsules in combination with pegylated alpha interferon and azathioprine to check you for these problems.
- Growth problems in children. Weight loss and slowed growth are common in children during combination treatment with ribavirin capsules and peginterferon alfa-2b or interferon alfa-2b. Most children will go through a growth spurt and gain weight after treatment stops. Some children may not reach the height that they were expected to have before treatment. Talk to your healthcare provider if you are concerned about your child’s growth during treatment with ribavirin capsules and peginterferon alfa-2b or with ribavirin capsules and interferon alfa-2b.
- Severe depression.
- Thoughts of hurting yourself or others, and suicide attempts. Adults and children who take ribavirin capsules, especially teenagers, are more likely to have suicidal thoughts or attempt to hurt themselves during treatment with ribavirin capsules. Call your healthcare provider right away or go to the nearest hospital emergency room if you have new or worse depression or thoughts about hurting yourself or others or dying.

The most common side effects of ribavirin capsules in adults include:

- flu-like symptoms - feeling tired or weak, headache, shaking chills along with high temperature (fever), nausea, and muscle aches
- mood changes, feeling irritable

The most common side effects of ribavirin capsules in children include:

- fever
- headache
- a decrease in blood cells that fight infection (neutropenia)
- tiredness
- decreased appetite
- vomiting

These are not all the possible side effects of ribavirin capsules. For more information ask your healthcare provider or pharmacist.

Call your doctor for medical advice about side effects. You may report side effects to FDA at 1-800-FDA-1088.

How should I store ribavirin capsules?

- Store ribavirin capsules at room temperature between 68°F to 77°F (20°C to 25°C).

Keep ribavirin capsules and all medicines out of the reach of children.

General information about the safe and effective use of ribavirin capsules.
It is not known if treatment with ribavirin capsules will cure hepatitis C virus infections or prevent cirrhosis, liver failure, or liver cancer that can be caused by hepatitis C virus infections.
It is not known if taking ribavirin capsules will prevent you from infecting another person with the hepatitis C virus.
Medicines are sometimes prescribed for purposes other than those listed in a Medication Guide. Do not use ribavirin capsules for a condition for which it was not prescribed. Do not give ribavirin capsules to other people, even if they have the same symptoms that you have. They may harm them.
You can ask your pharmacist or healthcare provider for information about ribavirin capsules that is written for health professionals.

What are the ingredients in ribavirin capsules?

Active ingredient: ribavirin

Inactive ingredients: microcrystalline cellulose, lactose monohydrate, povidone-K 30, and magnesium stearate. The capsule shell consists of titanium dioxide, sodium lauryl sulfate, and gelatin. The capsule is printed with edible ink containing black iron oxide.
For more information, call Aurobindo Pharma USA, Inc. at 1-866-850-2876.
Distributed by:
Aurobindo Pharma USA, Inc.
279 Princeton-Hightstown Road
East Windsor, NJ 08520
Manufactured by:
Aurobindo Pharma Limited
Hyderabad-500 032, India
This Medication Guide has been approved by the U.S. Food and Drug Administration.
Revised: 07/2023

PACKAGE LABEL-PRINCIPAL DISPLAY PANEL - 200 mg (500 Capsules Bottle)

NDC 65862-290-05
Rx only
Ribavirin Capsules USP
200 mg
PHARMACIST: Dispense the accompanying
Medication Guide to each patient.
AUROBINDO 500 Capsules